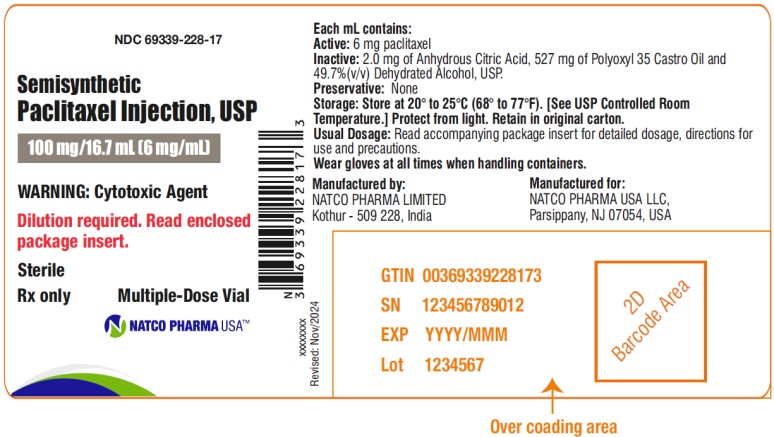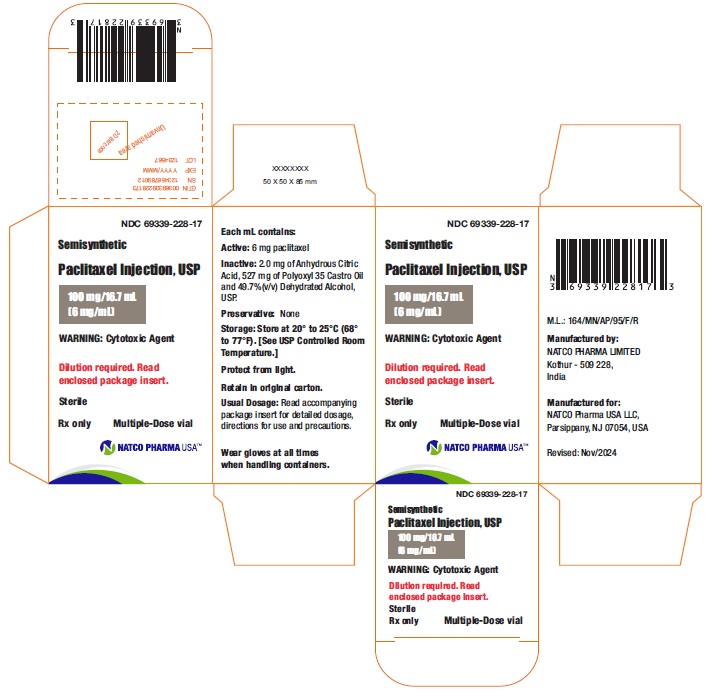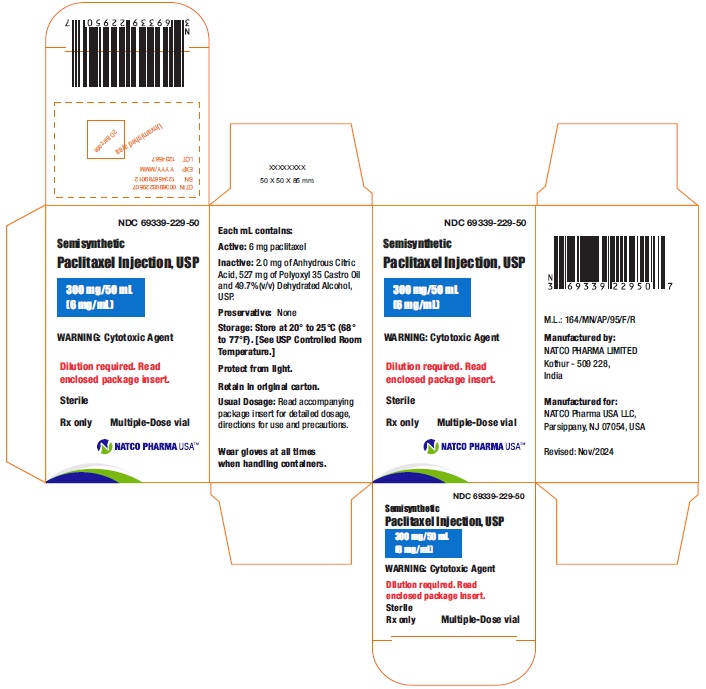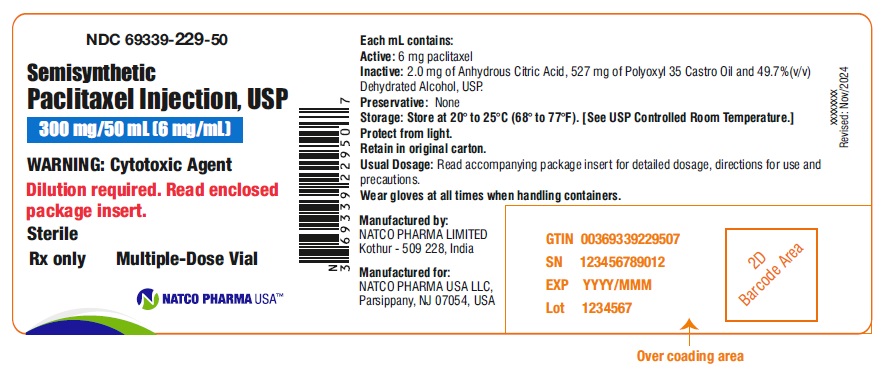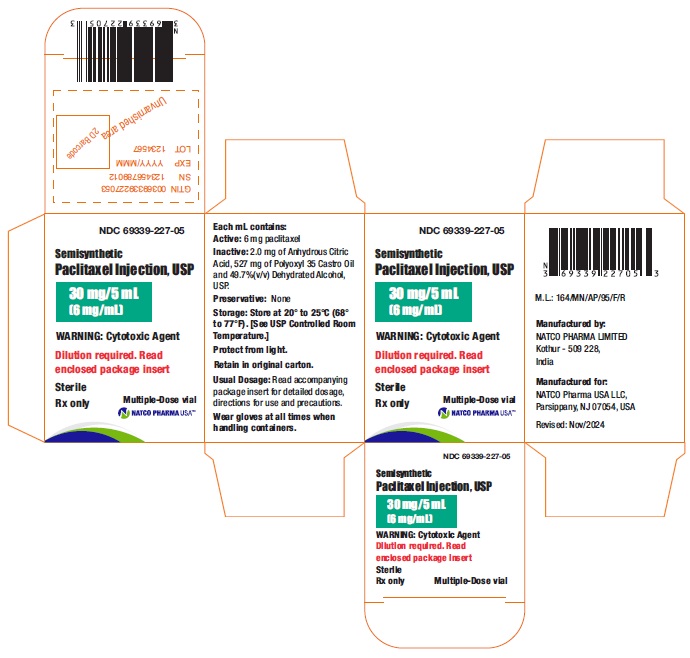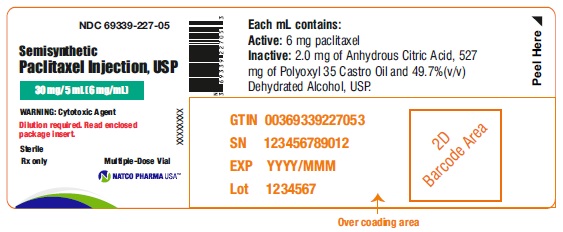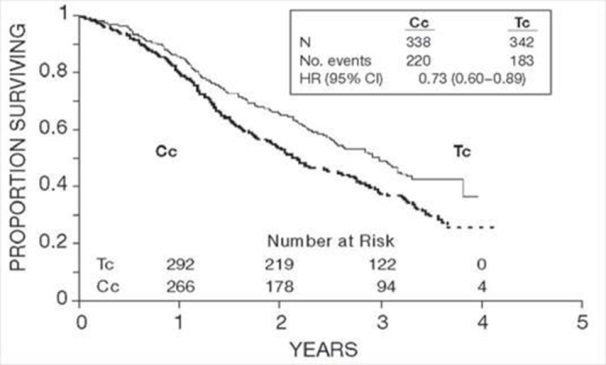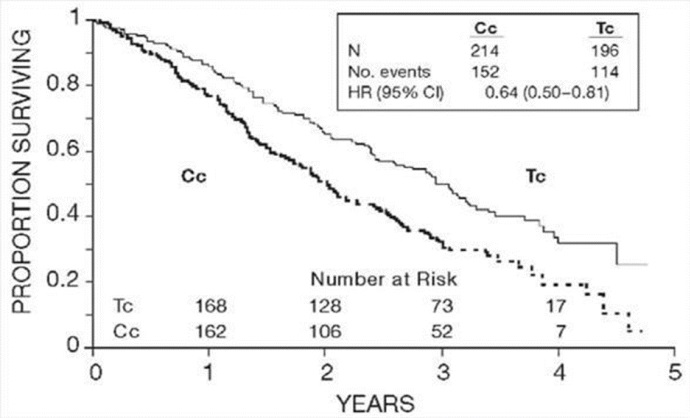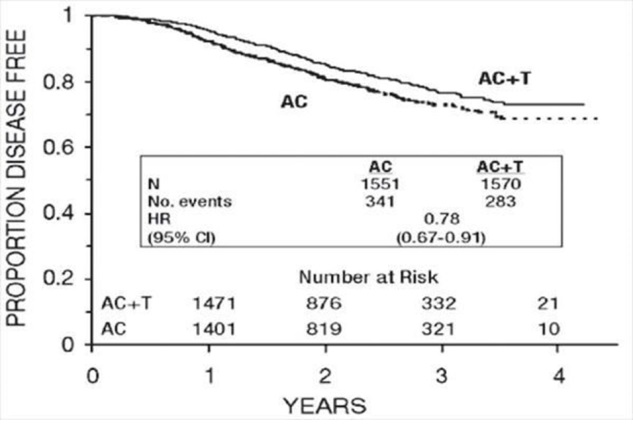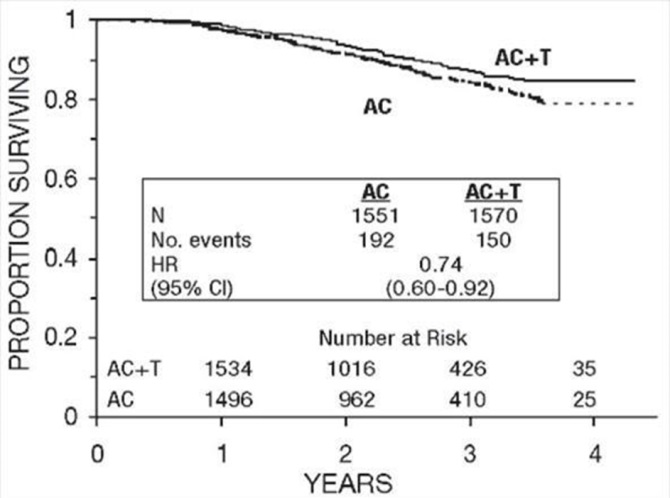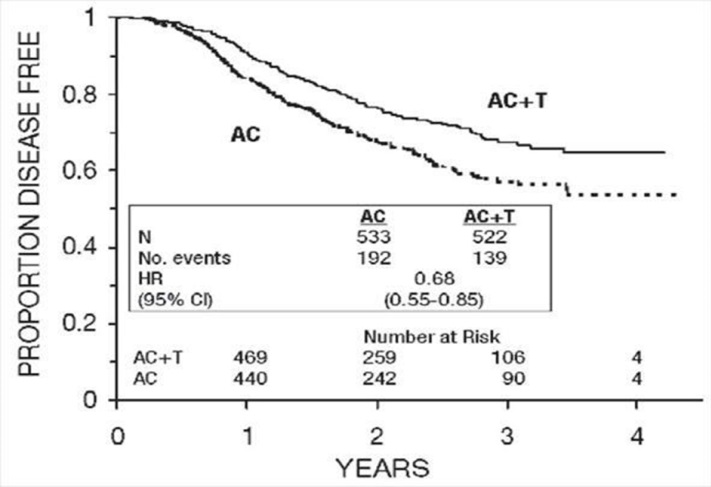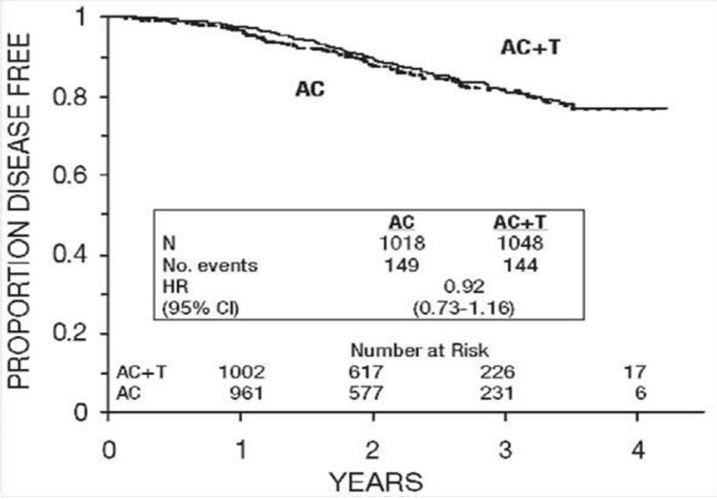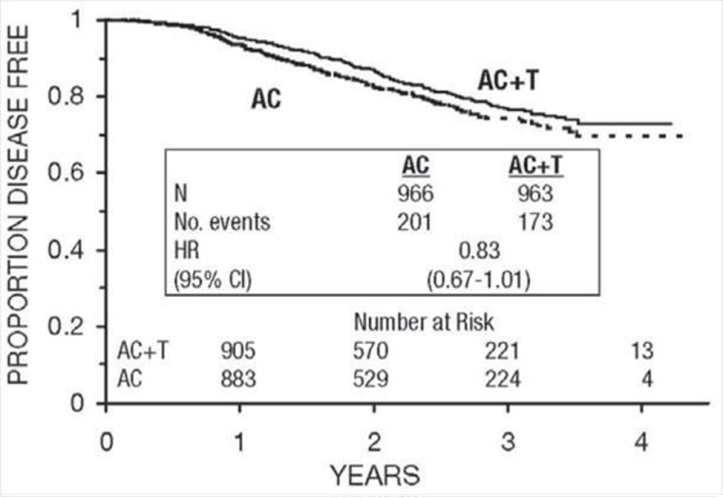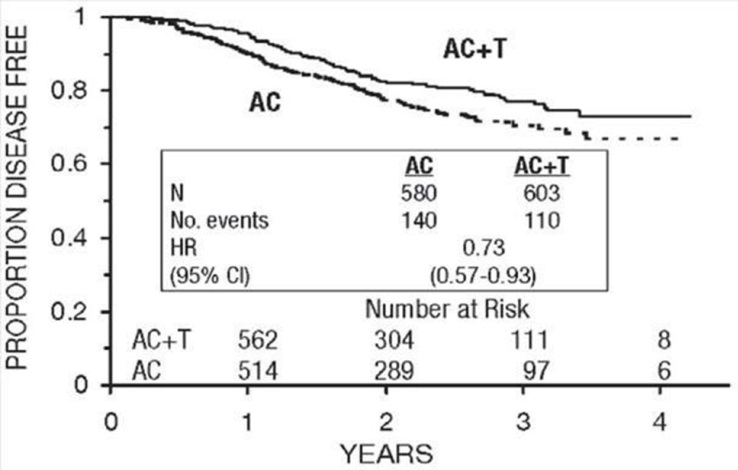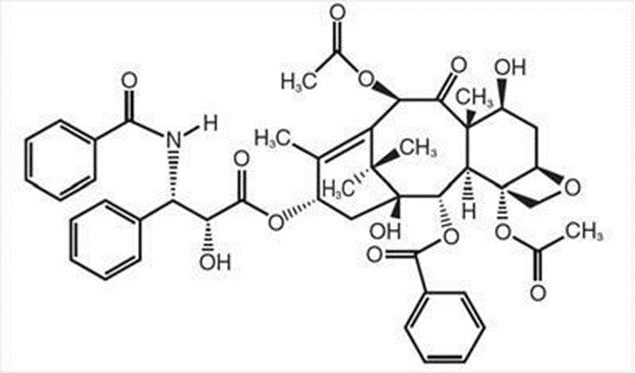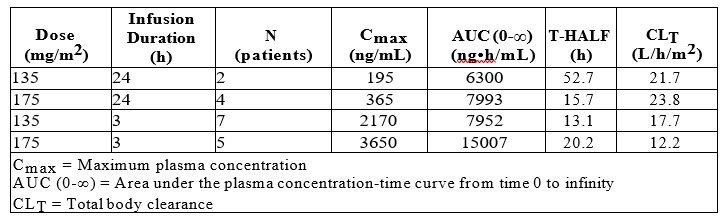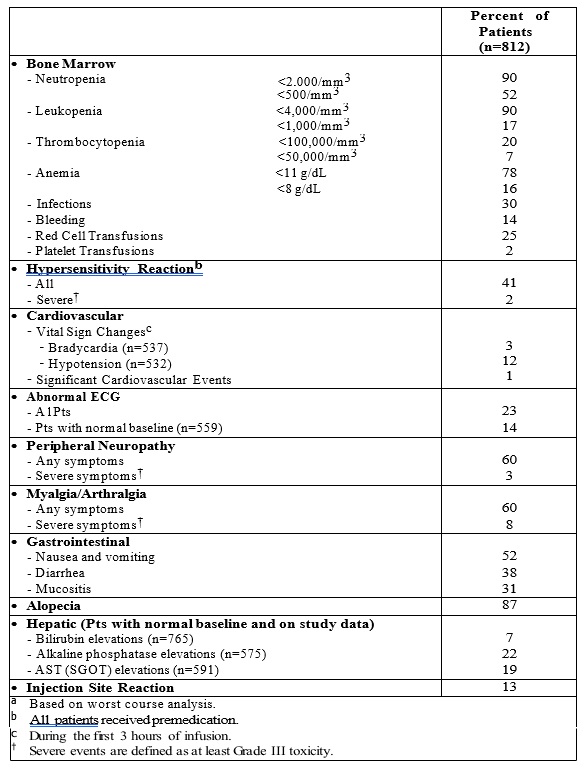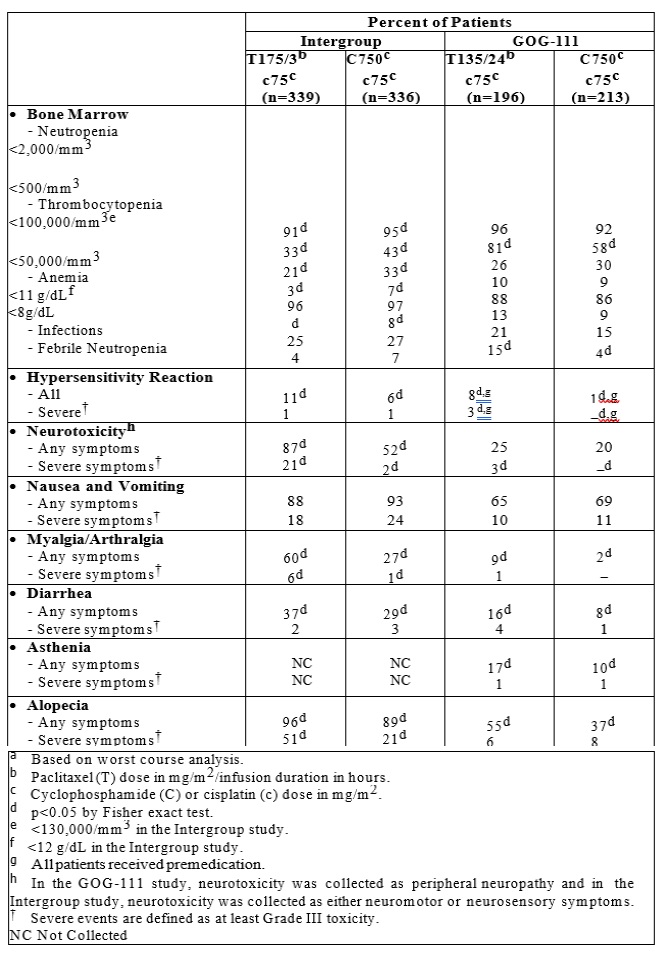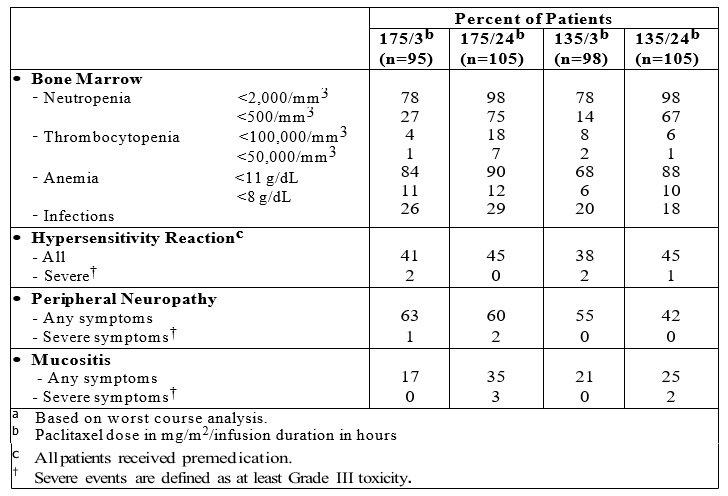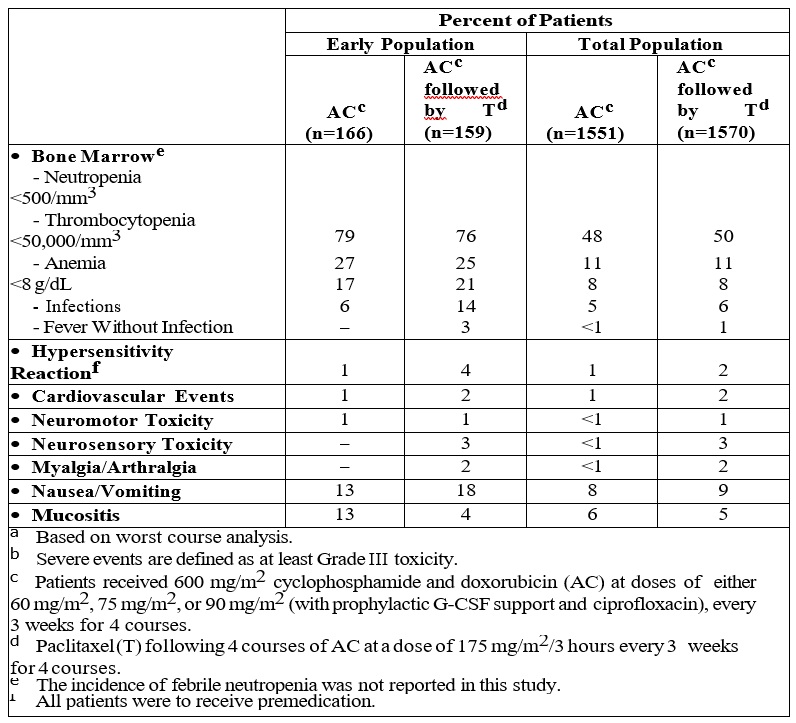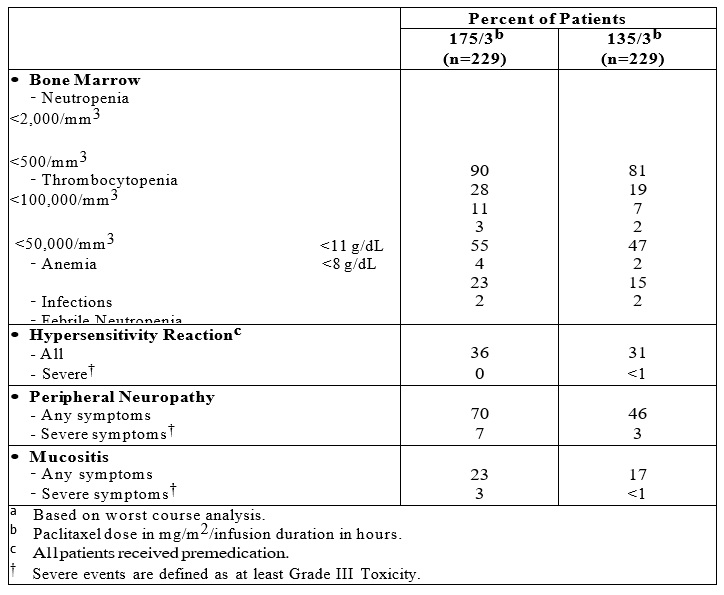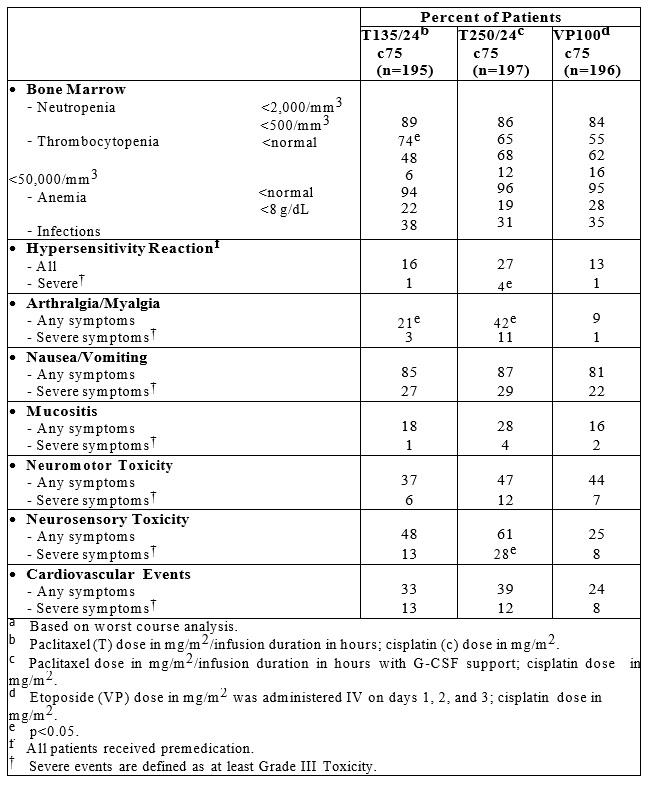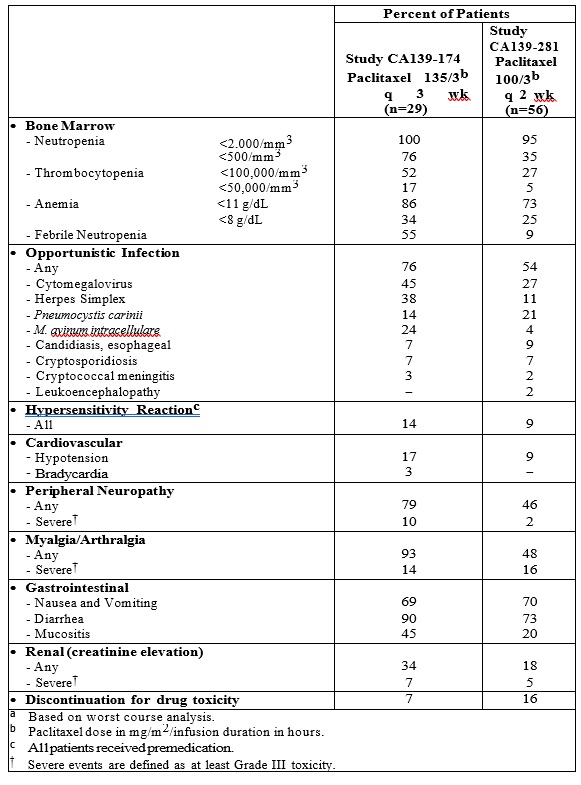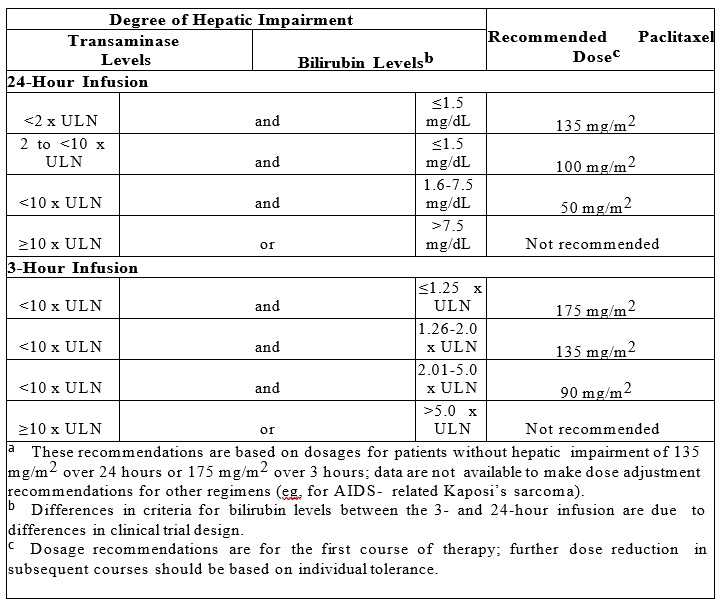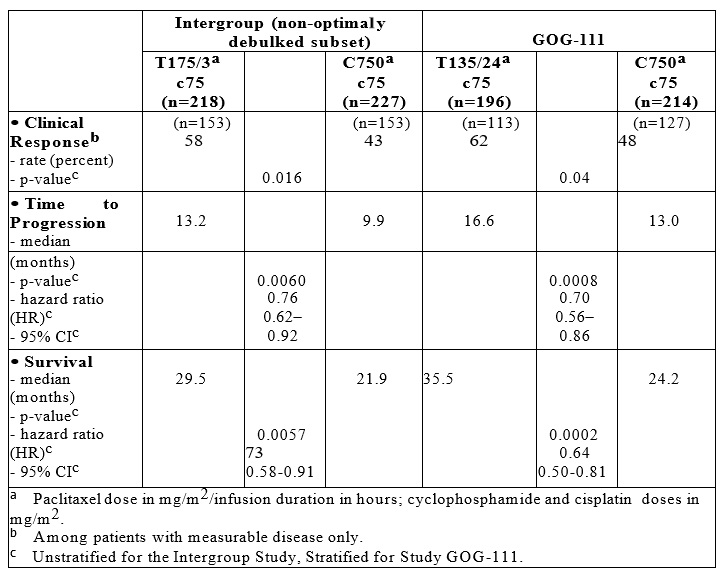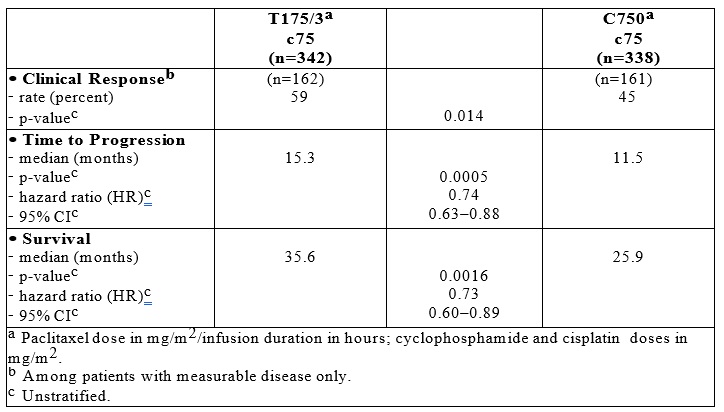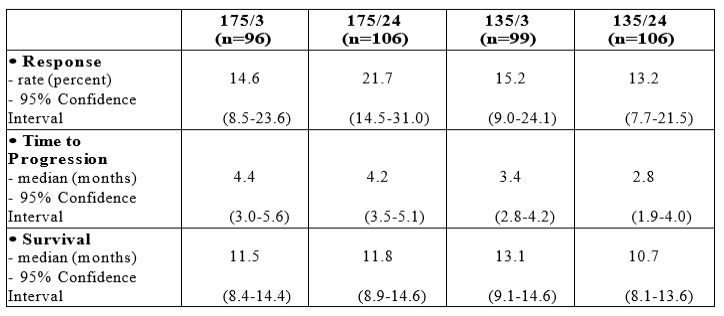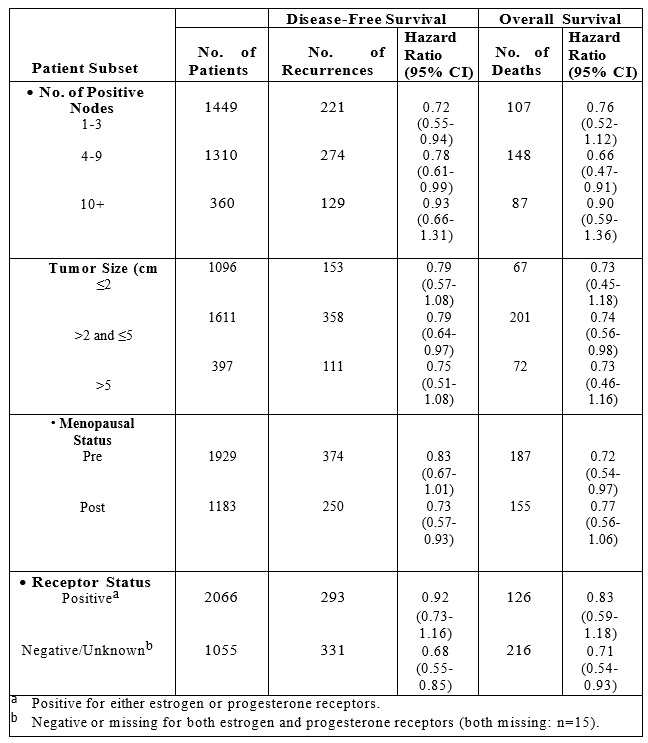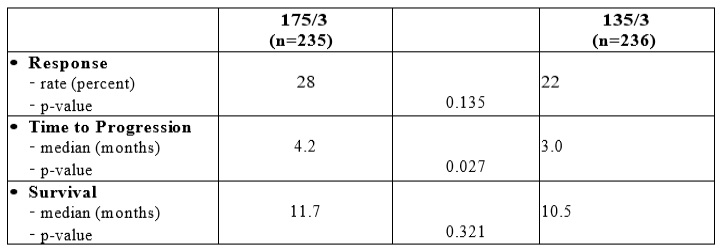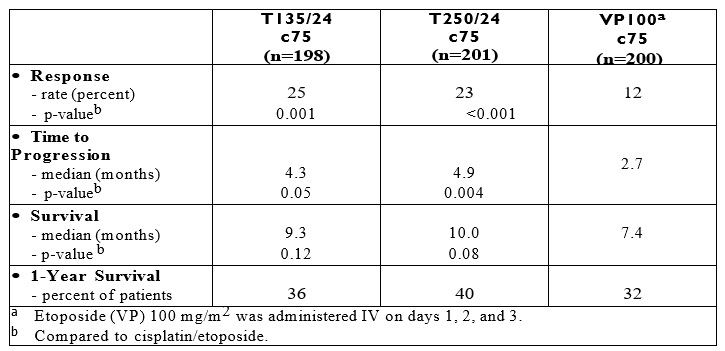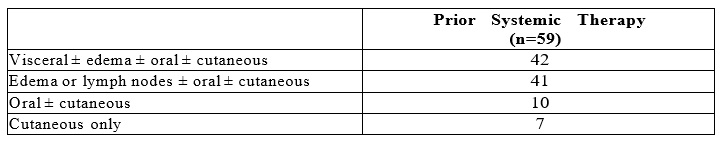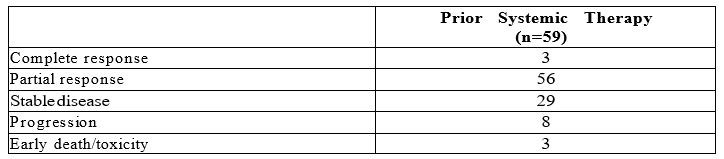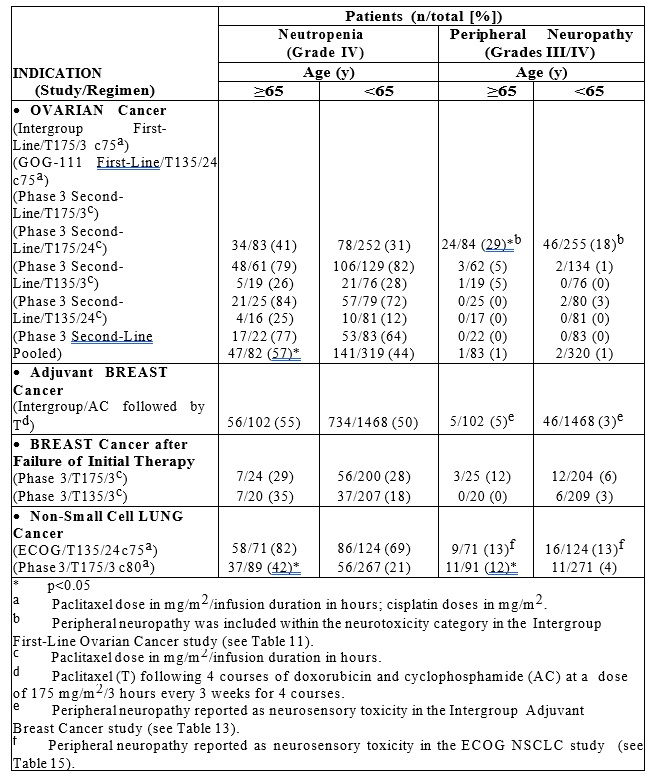 DRUG LABEL: Paclitaxel
NDC: 69339-227 | Form: INJECTION, SOLUTION
Manufacturer: Natco Pharma USA LLC
Category: prescription | Type: Human Prescription Drug Label
Date: 20260121

ACTIVE INGREDIENTS: PACLITAXEL 6 mg/1 mL
INACTIVE INGREDIENTS: POLYOXYL 35 CASTOR OIL; ALCOHOL; ANHYDROUS CITRIC ACID

Paclitaxel Injection, USP
(Patient Information Included)
Rx only

WARNING

Paclitaxel Injection, USP should be administered under the supervision of a physician experienced in the use of cancer chemotherapeutic agents. Appropriate management of complications is possible only when adequate diagnostic and treatment facilities are readily available.

Anaphylaxis and severe hypersensitivity reactions characterized by dyspnea and hypotension requiring treatment, angioedema, and generalized urticaria have occurred in 2%-4% of patients receiving paclitaxel in clinical trials. Fatal reactions have occurred in patients despite premedication. All patients should be pretreated with corticosteroids, diphenhydramine, and H2 antagonists. (See DOSAGE AND ADMINISTRATIONsection.) Patients who experience severe hypersensitivity reactions to paclitaxel should not be rechallenged with the drug.

Paclitaxel therapy should not be given to patients with solid tumors who have baseline neutrophil counts of less than 1,500 cells/mm^3 and should not be given to patients with AIDS-related Kaposi’s sarcoma if the baseline neutrophil count is less than 1,000 cells/mm^3. In order to monitor the occurrence of bone marrow suppression, primarily neutropenia, which may be severe and result in infection, it is recommended that frequent peripheral blood cell counts be performed on all patients receiving paclitaxel.

DESCRIPTION

Paclitaxel Injection, USP is a clear colorless to slightly ye low viscous solution. It is supplied as a nonaqueous solution intended for dilution with a suitable parenteral fluid prior to intravenous infusion. Paclitaxel is available in 30 mg (5 mL), 100 mg (16.7 mL), and 300 mg (50 mL) multiple-dose vials. Each mL of sterile nonpyrogenic solution contains 6 mg paclitaxel, 527 mg of Polyoxyl 35 Castor Oil, NF, 49.7% (v/v) Dehydrated Alcohol, USP and 2 mg Anhydrous Citric Acid, USP.

Paclitaxel is a natural product with antitumor activity. Paclitaxel is obtained via an extraction process from Taxus X media ‘Hicksii’. The chemical name for paclitaxel is (2aR,4S,4aS,6R,9S,11S,12S,12aR,12bS)-1,2a,3,4,4a,6,9,10,11,12,12a,12b-Dodecahydro-4,6,9,11,12,-12b-hexahydroxy-4a,8,13,13-tetramethyl-7,11-methano-5H- cyclodeca [3,4] benz [1,2-b] oxet-5-one 6,12b-diacetate, 12-benzoate, 9-ester with (2R,3S)-N-benzoyl-3-phenylisoserine.

Paclitaxel has the following structural formula:

Paclitaxel is a white to off-white crystal line powder with the empirical formula C47H51NO14 and a molecular weight of 853.9. It is highly lipophilic, insoluble in water, and melts at around 216-217°C.

CLINICAL PHARMACOLOGY

Paclitaxel is a novel antimicrotubule agent that promotes the assembly of microtubules from tubulin dimers and stabilizes microtubules by preventing depolymerization. This stability results in the inhibition of the normal dynamic reorganization of the microtubule network that is essential for vital interphase and mitotic cellular functions. In addition, paclitaxel induces abnormal arrays or “bundles” of microtubules throughout the cell cycle and multiple asters of microtubules during mitosis.

Following intravenous administration of paclitaxel, paclitaxel plasma concentrations declined in a biphasic manner. The initial rapid decline represents distribution to the peripheral compartment and elimination of the drug. The later phase is due, in part, to a relatively slow efflux of paclitaxel from the peripheral compartment.

Pharmacokinetic parameters of paclitaxel following 3- and 24-hour infusions of paclitaxel at dose levels of 135 and 175 mg/m^2 were determined in a Phase 3 randomized study in ovarian cancer patients and are summarized in the following table:

Table 1. Summary of Pharmacokinetic Parameters – Mean Values

It appeared that with the 24-hour infusion of paclitaxel, a 30% increase in dose (135 mg/m^2 versus 175 mg/m^2) increased the Cmax by 87%, whereas the AUC (0-∞) remained proportional. However, with a 3-hour infusion, for a 30% increase in dose, the Cmax and AUC (0-∞) were increased by 68% and 89%, respectively. The mean apparent volume of distribution at steady state, with the 24-hour infusion of paclitaxel, ranged from 227 to 688 L/m2, indicating extensive extravascular distribution and/or tissue binding of paclitaxel.

The pharmacokinetics of paclitaxel were also evaluated in adult cancer patients who received single doses of 15-135 mg/m^2 given by 1-hour infusions (n=15), 30-275 mg/m^2 given by 6-hour infusions (n=36), and 200-275 mg/m^2 given by 24-hour infusions (n=54) in Phase 1 & 2 studies. Values for CLT and volume of distribution were consistent with the findings in the Phase 3 study. The pharmacokinetics of paclitaxel in patients with AIDS-related Kaposi’s sarcoma have not been studied.

In vitro studies of binding to human serum proteins, using paclitaxel concentrations ranging from 0.1 to 50 μg/mL, indicate that between 89%-98% of drug is bound; the presence of cimetidine, ranitidine, dexamethasone, or diphenhydramine did not affect protein binding of paclitaxel.

After intravenous administration of 15-275 mg/m^2 doses of Paclitaxel Injection, USP as 1-, 6-, or 24-hour infusions, mean values for cumulative urinary recovery of unchanged drug ranged from 1.3% to 12.6% of the dose, indicating extensive non-renal clearance. In five patients administered a 225 or 250 mg/m^2 dose of radiolabeled paclitaxel as a 3- hour infusion, a mean of 71% of the radioactivity was excreted in the feces in 120 hours, and 14% was recovered in the urine. Total recovery of radioactivity ranged from 56% to 101% of the dose. Paclitaxel represented a mean of 5% of the administered radioactivity recovered in the feces, while metabolites, primarily 6α-hydroxypaclitaxel, accounted for the balance. In vitro studies with human liver microsomes and tissue slices showed that paclitaxel was metabolized primarily to 6α-hydroxypaclitaxel by the cytochrome P450 isozyme CYP2C8; and to two minor metabolites, 3’-p-hydroxypaclitaxel and 6α, 3’-p-dihydroxy-paclitaxel, by CYP3A4. In vitro, the metabolism of paclitaxel to 6α-hydroxypaclitaxel was inhibited by a number of agents (ketoconazole, verapamil, diazepam, quinidine, dexamethasone, cyclosporin, teniposide, etoposide, and vincristine), but the concentrations used exceeded those found in vivo following normal therapeutic doses. Testosterone, 17α-ethinyl estradiol, retinoic acid, and quercetin, a specific inhibitor of CYP2C8, also inhibited the formation of 6α-hydroxypaclitaxel in vitro. The pharmacokinetics of paclitaxel may also be altered in vivo as a result of interactions with compounds that are substrates, inducers, or inhibitors of CYP2C8 and/or CYP3A4. (See PRECAUTIONS: Drug Interactions section.)

The disposition and toxicity of paclitaxel 3-hour infusion were evaluated in 35 patients with varying degrees of hepatic function. Relative to patients with normal bilirubin, plasma paclitaxel exposure in patients with abnormal serum bilirubin ≤2 times upper limit of normal (ULN) administered 175 mg/m^2 was increased, but with no apparent increase in the frequency or severity of toxicity. In 5 patients with serum total bilirubin >2 times ULN, there was a statistically nonsignificant higher incidence of severe myelosuppression, even at a reduced dose (110 mg/m^2), but no observed increase in plasma exposure. (See PRECAUTIONS: Hepatic and DOSAGE AND ADMINISTRATION.) The effect of renal or hepatic dysfunction on the disposition of paclitaxel has not been investigated.

Possible interactions of paclitaxel with concomitantly administered medications have not been formally investigated.

CLINICAL STUDIES

Ovarian Carcinoma:

First-Line Data: The safety and efficacy of paclitaxel followed by cisplatin in patients with advanced ovarian cancer and no prior chemotherapy were evaluated in 2, Phase 3 multicentre, randomized, controlled trials. In an Intergroup study led by the European Organization for Research and Treatment of Cancer involving the Scandinavian Group NOCOVA, the National Cancer Institute of Canada, and the Scottish Group, 680 patients with Stage IIB–C, III, or IV disease (optimally or non-optimally debulked) received either paclitaxel 175 mg/m^2 infused over 3 hours followed by cisplatin 75 mg/m^2 (Tc) or cyclophosphamide 750 mg/m^2 followed by cisplatin 75 mg/m^2 (Cc) for a median of 6 courses. Although the protocol a lowed further therapy, only 15% received both drugs for 9 or more courses. In a study conducted by the Gynecological Oncology Group (GOG), 410 patients with Stage III or IV disease (>1 cm residual disease after staging laparotomy or distant metastases) received either paclitaxel 135 mg/m^2 infused over 24 hours followed by cisplatin 75 mg/m^2 or cyclophosphamide 750 mg/m^2 followed by cisplatin 75 mg/m^2 for 6 courses.

In both studies, patients treated with paclitaxel in combination with cisplatin had significantly higher response rate, longer time to progression, and longer survival time compared with standard therapy. These differences were also significant for the subset of patients in the Intergroup study with non-optimally debulked disease, although the study was not fully powered for subset analyses (Tables 2A and 2B). Kaplan- Meier survival curves for each study are shown in Figures 1 and 2.

Table 2A. Efficacy in the Phase 3 First-Line Ovarian Carcinoma Studies

Table 2B. Efficacy in the Phase 3 First-Line Ovarian Carcinoma Intergroup Study

Figure 1. Survival: Cc Versus Tc (Intergroup)

Figure 2. Survival: Cc Versus Tc (GOG-111)

The adverse event profile for patients receiving paclitaxel in combination with cisplatin in these studies was qualitatively consistent with thatseen for the pooled analysis of data from 812 patients treated with single-agent paclitaxel in 10 clinical studies. These adverse events and adverse events from the Phase 3 first-line ovarian carcinoma studies are described in the ADVERSE REACTIONS section in tabular (Tables 10 and 11) and narrative form.

Second-Line Data: Data from five Phase 1 & 2 clinical studies (189 patients), a multicenter randomized Phase 3 study (407patients), as we l as aninterim analysis of data from more than300 patients enrolledin a treatment referral center program were usedinsupport of the use of paclitaxel in patients who have failedinitial or subsequent chemotherapy for metastatic carcinoma of the ovary. Two of the Phase 2 studies (92 patients) utilized an initial dose of 135 to 170 mg/m^2 in most patients (>90%) administeredover 24hours by continuous infusion. Response rates inthese two studies were 22% (95% CI: 11% to 37%) and 30% (95% CI: 18% to 46%) with a total of 6 complete and18 partial responses in 92 patients. The median durationof overall response in these two studies measured from the first day of treatment was 7.2 months (range: 3.5-15.8 months) and 7.5 months (range: 5.3-17.4 months), respectively. The median survival was 8.1 months (range: 0.2-36.7 months) and 15.9 months (range: 1.8-34.5+ months).

The Phase 3 study had a bifactorial designandcomparedthe efficacy andsafety of paclitaxel, administered at two different doses (135 or 175 mg/m^2 and schedules (3- or 24-hour infusion). The overall response rate for the 407 patients was 16.2% (95% CI: 12.8% to 20.2%), with 6 complete and 60 partial responses. Duration of response, measured from the first day of treatment was 8.3 months (range: 3.2-21.6 months). Median time to progression was 3.7 months (range: 0.1+ - 25.1+ months). Median survival was 11.5 months (range: 0.2-26.3+ months).

Response rates, median survival, and median time to progression for the 4 arms are given in the following table.

Table 3. Efficacy in the Phase 3 Second-Line Ovarian Carcinoma Study

Analyses were performed as planned by the bifactorial study design described in the protocol, by comparing the two doses (135 or 175 mg/m^2) irrespective of the schedule (3 or 24 hours) and the two schedules irrespective of dose. Patients receiving the 175 mg/m^2 dose had a response rate similar to that for those receiving the 135 mg/m^2 dose: 18% vs. 14% (p=0.28). No difference in response rate was detected when comparing the 3-hour with the 24-hour infusion: 15% vs. 17% (p=0.50). Patients receiving the 175 mg/m^2 dose of paclitaxel had a longer time to progression than those receiving the 135 mg/m^2 dose: median 4.2 vs. 3.1 months (p=0.03). The median time to progression for patients receiving the 3-hour vs. the 24-hour infusion was 4.0 months vs. 3.7 months, respectively. Median survival was 11.6 months in patients receiving the 175 mg/m^2 dose of paclitaxel and 11.0 months in patients receiving the 135 mg/m^2 dose (p=0.92).

Median survival was 11.7 months for patients receiving the 3-hour infusion of paclitaxel and 11.2 months for patients receiving the 24 hour infusion (p=0.91). These statistical analyses should be viewed with caution because of the multiple comparisons made.

Paclitaxel remained active in patients who had developed resistance to platinum- containing therapy (defined as tumor progression while on, or tumor relapse within 6 months from completion of, a platinum-containing regimen) with response rates of 14% in the Phase 3 study and 31% in the Phase 1 & 2 clinical studies.

The adverse event profile in this Phase 3 study was consistent with that seen for the pooled analysis of data from 812 patients treated in 10 clinical studies. These adverse events and adverse events from the Phase 3 second-line ovarian carcinoma study are described in the ADVERSE REACTIONS section in tabular (Tables 10 and 12) and narrative form.

The results of this randomized study support the use of Paclitaxel Injection, USP at doses of 135 to 175 mg/m^2, administered by a 3-hour intravenous infusion. The same doses administered by 24-hour infusion were more toxic. However, the study had insufficient power to determine whether a particular dose and schedule produced superior efficacy.

Breast Carcinoma:

Adjuvant Therapy

A Phase 3 Intergroup study (Cancer and Leukemia Group B [CALGB], Eastern Cooperative Oncology Group [ECOG], North Central Cancer Treatment Group [NCCTG], and Southwest Oncology Group [SWOG]) randomized 3170 patients with node-positive breast carcinoma to adjuvant therapy with paclitaxel or to no further chemotherapy following 4 courses of doxorubicin and cyclophosphamide (AC). This multicenter trial was conducted in women with histologically positive lymph nodes following either a mastectomy or segmental mastectomy and nodal dissections. The 3 x 2 factorial study was designed to assess the efficacy and safety of 3 different dose levels of doxorubicin (A) and to evaluate the effect of the addition of paclitaxel administered following the completion of AC therapy. After stratification for the number of positive lymph nodes (1– 3, 4–9, or 10+), patients were randomized to receive cyclophosphamide at a dose of 600 mg/m^2 and doxorubicin at doses of either 60 mg/m^2 (on day 1), 75 mg/m^2 (in 2 divided doses on days 1 and 2), or 90 mg/m^2 (in 2 divided doses on days 1 and 2 with prophylactic G-CSF support and ciprofloxacin) every 3 weeks for 4 courses and either paclitaxel 175 mg/m^2 as a 3-hour infusion every 3 weeks for 4 additional courses or no additional chemotherapy. Patients whose tumors were positive were to receive subsequent tamoxifen treatment (20 mg daily for 5 years); patients who received segmental mastectomies prior to study were to receive breast irradiation after recovery from treatment-related toxicities.

At the time of the current analysis, median follow-up was 30.1 months. Of the 2066 patients who were hormone receptor positive, 93% received tamoxifen. The primary analyses of disease-free survival and overall survival used multivariate Cox models, which included paclitaxel administration, doxorubicin dose, number of positive lymph nodes, tumor size, menopausal status, and estrogen receptor status as factors. Based on the model for disease-free survival, patients receiving AC followed by paclitaxel had a 22% reduction in the risk of disease recurrence compared to patients randomized to AC alone (Hazard Ratio [HR]=0.78, 95% Cl, 0.67–0.91, p=0.0022). They also had a 26% reduction in the risk of death (HR=0.74, 95% CI, 0.60–0.92, p=0.0065). For disease-free survival and overall survival, p-values were not adjusted for interim analyses. Kaplan- Meier curves are shown in Figures 3 and 4. Increasing the dose of doxorubicin higher than 60 mg/m^2 had no effect on either disease-free survival or overall survival.

Figure 3. Disease-Free Survival: ac Versus AC+T

F igure 4. Survival: AC Versus AC+T

Subset analyses: Subsets defined by variables of known prognostic importance in adjuvant breast carcinoma were examined, including number of positive lymph nodes, tumor size, hormone receptor status, and menopausal status. Such analyses must be interpreted with care, as the most secure finding is the overall study result. In general, a reduction in hazard similar to the overall reduction was seen with paclitaxel for both disease-free and overall survival in all of the larger subsets with one exception; patients with receptor-positive tumors had a smaller reduction in hazard (HR=0.92) for disease- free survival with paclitaxel than other groups. Results of subset analyses are shown in Table 4.

Table 4. Subset Analyses — Adjuvant Breast Carcinoma Study

These retrospective subgroup analyses suggest that the beneficial effect of paclitaxel is clearly established in the receptor-negative subgroup, but the benefit in receptor- positive patients is not yet clear. With respect to menopausal status, the benefit of paclitaxel is consistent (see Table 4 and Figures 5–8).

Figure 5. Disease-Free Survival: Receptor Status Negative/Unknown AC Versus AC+T

Figure 6. Disease-Free Survival: Receptor Status Positive AC Versus AC+T

Figure 7. Disease-Free Survival: Premenopausal AC Versus AC+T

Figure 8. Disease-Free Survival: Postmenopausal AC Versus AC+T

The adverse event profile for the patients who received paclitaxel subsequent to AC was consistent with that seen in the pooled analysis of data from 812 patients (Table 10) treated with single-agent paclitaxel in 10 clinical studies. These adverse events are described in the ADVERSE REACTIONS section in tabular (Tables 10 and 13) and narrative form.

After Failure of Initial Chemotherapy:

Data from 83 patients accrued in three Phase 2 open label studies and from 471 patients enrolled in a Phase 3 randomized study were available to support the use of paclitaxel in patients with metastatic breast carcinoma.

Phase 2 Open Label Studies: Two studies were conducted in 53 patients previously treated with a maximum of one prior chemotherapeutic regimen. Paclitaxel was administered in these two trials as a 24-hour infusion at initial doses of 250 mg/m^2 (with G-CSF support) or 200 mg/m^2. The response rates were 57% (95% CI: 37% to 75%) and 52% (95% CI: 32% to 72%), respectively. The third Phase 2 study was conducted in extensively pretreated patients who had failed anthracycline therapy and who had received a minimum of two chemotherapy regimens for the treatment of metastatic disease. The dose of paclitaxel was 200 mg/m^2 as a 24-hour infusion with G-CSF support. Nine of 30 patients achieved a partial response, for a response rate of 30% (95% CI: 15% to 50%).

Phase 3 Randomized Study: This multicenter trial was conducted in patients previously treated with one or two regimens of chemotherapy. Patients were randomized to receive paclitaxel at a dose of either 175 mg/m^2 or 135 mg/m^2 given as a 3-hour infusion. In the 471 patients enrolled, 60% had symptomatic disease with impaired performance status at study entry, and 73% had visceral metastases. These patients had failed prior chemotherapy either in the adjuvant setting (30%), the metastatic setting (39%), or both (31%). Sixty-seven percent of the patients had been previously exposed to anthracyclines and 23% of them had disease considered resistant to this class of agents.

The overall response rate for the 454 evaluable patients was 26% (95% CI: 22% to 30%), with 17 complete and 99 partial responses. The median duration of response, measured from the first day of treatment, was 8.1 months (range: 3.4-18.1+ months). Overall for the 471 patients, the median time to progression was 3.5 months (range: 0.03-17.1 months). Median survival was 11.7 months (range: 0-18.9 months).

Response rates, median survival and median time to progression for the 2 arms are given in the following table.

Table 5. Efficacy in Breast Cancer after Failure of Initial Chemotherapy or Within 6 Months of Adjuvant Chemotherapy

The adverse event profile of the patients who received single-agent Paclitaxel Injection, USP, in the Phase 3 study was consistent with that seen for the pooled analysis of data from 812 patients treated in 10 clinical studies. These adverse events and adverse events from the Phase 3 breast carcinoma study are described in the ADVERSE REACTIONS section in tabular (Tables 10 and 14) and narrative form.

Non-Small Cell Lung Carcinoma (NSCLC)

In a Phase 3 open-label randomized study conducted by the ECOG, 599 patients were randomized to either paclitaxel (T) 135 mg/m^2 as a 24-hour infusion in combination with cisplatin (c) 75 mg/m^2, paclitaxel (T) 250 mg/m^2 as a 24-hour infusion in combination with cisplatin (c) 75 mg/m^2 with G-CSF support, or cisplatin (c) 75 mg/m^2 on day 1, followed by etoposide (VP) 100 mg/m^2 on days 1, 2, and 3 (control). Response rates, median time to progression, median survival, and 1-year survival rates are given in the following table. The reported p-values have not been adjusted for multiple comparisons. There were statistically significant differences favoring each of the paclitaxel plus cisplatin arms for response rate and time to tumor progression. There was no statistically significant difference in survival between either paclitaxel plus cisplatin arm and the cisplatin plus etoposide arm.

Table 6. Efficacy Parameters in the Phase 3 First-Line NSCLC Study

In the ECOG study, the Functional Assessment of Cancer Therapy-Lung (FACT-L) questionnaire had 7 subscales that measured subjective assessment of treatment. Of the 7, the Lung Cancer Specific Symptoms subscale favored the paclitaxel 135 mg/m^2/24 hour plus cisplatin arm compared to the cisplatin/etoposide arm. For all other factors, there was no difference in the treatment groups.

The adverse event profile for patients who received paclitaxel in combination with cisplatin in this study was generally consistent with that seen for the pooled analysis of data from 812 patients treated with single-agent paclitaxel in 10 clinical studies. These adverse events and adverse events from the Phase 3 first-line NSCLC study are described in the ADVERSE REACTIONS section in tabular (Tables 10 and 15) and narrative form.

AIDS-Related Kaposis & Sarcoma:

Data from 2, Phase 2 open-label studies support the use of paclitaxel as second-line therapy in patients with AIDS-related Kaposi’s sarcoma. Fifty-nine of the 85 patients enrolled in these studies had previously received systemic therapy, including interferon alpha (32%), DaunoXome® (31%), DOXIL® (2%), and doxorubicin containing chemotherapy (42%), with 64% having received prior anthracyclines. Eighty-five percent of the pretreated patients had progressed on, or could not tolerate, prior systemic therapy.1
In Study CA139-174, patients received paclitaxel at 135 mg/m^2 as a 3-hour infusion every 3 weeks (intended dose intensity 45 mg/m^2/week). If no dose-limiting toxicity was observed, patients were to receive 155 mg/m^2 and 175 mg/m^2 in subsequent courses. Hematopoietic growth factors were not to be used initially. In Study CA139-281, patients received paclitaxel at 100 mg/m^2 as a 3-hour infusion every 2 weeks (intended dose intensity 50 mg/m^2/week). In this study patients could be receiving hematopoietic growth factors before the start of paclitaxel therapy, or this support was to be initiated as indicated; the dose of paclitaxel was not increased. The dose intensity of paclitaxel used in this patient population was lower than the dose intensity recommended for other solid tumors.

All patients had widespread and poor-risk disease. Applying the ACTG staging criteria to patients with prior systemic therapy, 93% were poor risk for extent of disease (T1), 88% had a CD4 count <200 cells/mm3 (I1), and 97% had poor risk considering their systemic illness (S1).

All patients in Study CA139-174 had a Karnofsky performance status of 80 or 90 at baseline; in Study CA139-281, there were 26 (46%) patients with a Karnofsky performance status of 70 or worse at baseline.

Table 7. Extent of Disease at Study Entry Percent of Patients

Although the planned dose intensity in the 2 studies was slightly different (45 mg/m^2/week in Study CA139-174 and 50 mg/m^2/week in Study CA139-281), delivered dose intensity was 38 to 39 mg/m^2/week in both studies, with a similar range (20–24 to 51–61).

Efficacy: The efficacy of paclitaxel was evaluated by assessing cutaneous tumor response according to the amended ACTG criteria and by seeking evidence of clinical benefit in patients in 6 domains of symptoms and/or conditions that are commonly related to AIDS-related Kaposi’s sarcoma.

Cutaneous Tumor Response (Amended ACTG Criteria): The objective response rate was 59% (95% CI, 46–72%) (35 of 59 patients) in patients with prior systemic therapy. Cutaneous responses were primarily defined as flattening of more than 50% of previously raised lesions.

Table 8. Overall Best Response (Amended ACTG Criteria) Percent of Patients

The median time to response was 8.1 weeks and the median duration of response measured from the first day of treatment was 10.4 months (95% CI, 7.0–11.0 months) for the patients who had previously received systemic therapy. The median time to progression was 6.2 months (95% CI, 4.6–8.7 months).

Additional Clinical Benefit: Most data on patient benefit were assessed retrospectively (plans for such analyses were not included in the study protocols). Nonetheless, clinical descriptions and photographs indicated clear benefit in some patients, including instances of improved pulmonary function in patients with pulmonary involvement, improved ambulation, resolution of ulcers, and decreased analgesic requirements in patients with Kaposi’s sarcoma (KS) involving the feet and resolution of facial lesions and edema in patients with KS involving the face, extremities, and genitalia.

Safety: The adverse event profile of paclitaxel administered to patients with advanced HIV disease and poor-risk AIDS-related Kaposi’s sarcoma was generally similar to that seen in the pooled analysis of data from 812 patients with solid tumors. These adverse events and adverse events from the Phase 2 second-line Kaposi’s sarcoma studies are described in the ADVERSE REACTIONS section in tabular (Tables 10 and 16) and narrative form. In this immunosuppressed patient population, however, a lower dose intensity of paclitaxel and supportive therapy including hematopoietic growth factors in patients with severe neutropenia are recommended. Patients with AIDS-related Kaposi’s sarcoma may have more severe hematologic toxicities than patients with solid tumors.

INDICATIONS & USAGE

Paclitaxel Injection, USP is indicated as subsequent therapy for the treatment of advanced carcinoma of the ovary. As first-line therapy, paclitaxel is indicated in combination with cisplatin.

Paclitaxel is indicated for the adjuvant treatment of node-positive breast cancer administered sequentially to standard doxorubicin-containing combination chemotherapy. In the clinical trial, there was an overall favorable effect on disease-free and overall survival in the total population of patients with receptor-positive and receptor-negative tumors, but the benefit has been specifically demonstrated by available data (median follow-up 30 months) only in the patients with estrogen and progesterone receptornegative tumors. (See CLINICAL STUDIES: Breast Carcinoma.)

Paclitaxel Injection, USP is indicated for the treatment of breast cancer after failure of combination chemotherapy for metastatic disease or relapse within 6 months of adjuvant chemotherapy. Prior therapy should have included an anthracycline unless clinically contraindicated.

Paclitaxel, in combination with cisplatin, is indicated for the first-line treatment of nonsmall cell lung cancer in patients who are not candidates for potentially curative surgery and/or radiation therapy.

Paclitaxel is indicated for the second-line treatment of AIDS-related Kaposi’s sarcoma.

CONTRAINDICATIONS

Paclitaxel Injection, USP is contraindicated in patients who have a history of hypersensitivity reactions to paclitaxel or other drugs formulated in Polyoxyl 35 Castor Oil, NF.

Paclitaxel Injection, USP should not be used in patients with solid tumors who have baseline neutrophil counts of <1,500 cells/mm^3 or in patients with AIDS-related Kaposi’s sarcoma with baseline neutrophil counts of <1,000 cells/mm^3.

WARNINGS

Anaphylaxis and severe hypersensitivity reactions characterized by dyspnea and hypotension requiring treatment, angioedema, and generalized urticaria have occurred in 2%-4% of patients receiving paclitaxel in clinical trials. Fatal reactions have occurred in patients despite premedication. All patients should be pretreated with corticosteroids, diphenhydramine, and H2 antagonists. (See DOSAGE AND ADMINISTRATION section.) Patients who experience severe hypersensitivity reactions to paclitaxel should not be rechallenged with the drug.

Bone marrow suppression (primarily neutropenia) is dose-dependent and is the dose- limiting toxicity. Neutrophil nadirs occurred at a median of 11 days. Paclitaxel should not be administered to patients with baseline neutrophil counts of less than 1,500 cells/mm^3 (<1,000 cells/mm^3 for patients with KS). Frequent monitoring of blood counts should be instituted during paclitaxel treatment. Patients should not be re-treated with subsequent cycles of paclitaxel until neutrophils recover to a level >1,500 cells/mm^3 (>1,000 cells/mm^3 for patients with KS) and platelets recover to a level >100,000 cells/mm^3.

Severe conduction abnormalities have been documented in <1% of patients during paclitaxel therapy and in some cases requiring pacemaker placement. If patients develop significant conduction abnormalities during paclitaxel infusion, appropriate therapy should be administered and continuous cardiac monitoring should be performed during subsequent therapy with paclitaxel.

Pregnancy: Paclitaxel can cause fetal harm when administered to a pregnant woman. Administration of paclitaxel during the period of organogenesis to rabbits at doses of 3.0 mg/kg/day (about 0.2 the daily maximum recommended human dose on a mg/m^2 basis) caused embryo- and fetotoxicity, as indicated by intrauterine mortality, increased resorptions, and increased fetal deaths. Maternal toxicity was also observed at this dose. No teratogenic effects were observed at 1.0 mg/kg/day (about 1/15 the daily maximum recommended human dose on a mg/m^2 basis); teratogenic potential could not be assessed at higher doses due to extensive fetal mortality.

There are no adequate and well-controlled studies in pregnant women. If paclitaxel is used during pregnancy, or if the patient becomes pregnant while receiving this drug, the patient should be apprised of the potential hazard to the fetus. Women of childbearing potential should be advised to avoid becoming pregnant.

PRECAUTIONS

Contact of the undiluted concentrate with plasticized polyvinyl chloride (PVC) equipment or devices used to prepare solutions for infusion is not recommended. In order to minimize patient exposure to the plasticizer DEHP [di-(2-ethylhexyl) phthalate], which may be leached from PVC infusion bags or sets, diluted Paclitaxel Injection, USP solutions should preferably be stored in bottles (glass, polypropylene) or plastic bags (polypropylene, polyolefin) and administered through polyethylene-lined administration sets.

Paclitaxel should be administered through an in-line filter with a microporous membrane not greater than 0.22 microns. Use of filter devices such as IVEX-2® filters which incorporate short inlet and outlet PVC-coated tubing has not resulted in significant leaching of DEHP.

Drug Interactions:

In a Phase I trial using escalating doses of paclitaxel (110-200 mg/m^2) and cisplatin (50 or 75 mg/m^2) given as sequential infusions, myelosuppression was more profound when paclitaxel was given after cisplatin than with the alternate sequence (i.e., paclitaxel before cisplatin). Pharmacokinetic data from these patients demonstrated a decrease in paclitaxel clearance of approximately 33% when paclitaxel was administered following cisplatin.

The metabolism of paclitaxel is catalyzed by cytochrome P450 isoenzymes CYP2C8 and CYP3A4. In the absence of formal clinical drug interaction studies, caution should be exercised when administering paclitaxel concomitantly with known substrates or inhibitors of the cytochrome P450 isoenzymes CYP2C8 and CYP3A4. Caution should be exercised when paclitaxel is concomitantly administered with known substrates (eg, midazolam, buspirone, felodipine, lovastatin, eletriptan, sildenafil, simvastatin, and triazolam), inhibitors (eg, atazanavir, clarithromycin, indinavir, itraconazole, ketoconazole, nefazodone, nelfinavir, ritonavir, saquinavir, and telithromycin), and inducers (eg, rifampin and carbamazepine) of CYP3A4. (See CLINICAL PHARMACOLOGY section.)

Caution should also be exercised when paclitaxel is concomitantly administered with known substrates (eg, repaglinide and rosiglitazone), inhibitors (eg, gemfibrozil), and inducers (eg, rifampin) of CYP2C8. (See CLINICAL PHARMACOLOGY.)

Potential interactions between paclitaxel, a substrate of CYP3A4, and protease inhibitors (ritonavir, saquinavir, indinavir, and nelfinavir), which are substrates and/or inhibitors of CYP3A4, have not been evaluated in clinical trials.

Reports in the literature suggest that plasma levels of doxorubicin (and its active metabolite doxorubicinol) may be increased when paclitaxel and doxorubicin are used in combination.

Hematology:

Paclitaxel therapy should not be administered to patients with baseline neutrophil counts of less than 1,500 cells/mm^3. In order to monitor the occurrence of myelotoxicity, it is recommended that frequent peripheral blood cell counts be performed on all patients receiving paclitaxel. Patients should not be retreated with subsequent cycles of paclitaxel until neutrophils recover to a level >1,500 cells/mm^3 and platelets recover to a level >100,000 cells/mm^3. In the case of severe neutropenia (<500 cells/mm^3 for seven days or more) during a course of paclitaxel therapy, a 20% reduction in dose for subsequent courses of therapy is recommended.

For patients with advanced HIV disease and poor-risk AIDS-related Kaposi’s sarcoma, paclitaxel, at the recommended dose for this disease, can be initiated and repeated if the neutrophil count is at least 1,000 cells/mm^3.

Hypersensitivity Reactions:

Patients with a history of severe hypersensitivity reactions to products containing Polyoxyl 35 Castor Oil, NF (e.g., cyclosporin for injection concentrate and teniposide for injection concentrate) should not be treated with paclitaxel. In order to avoid the occurrence of severe hypersensitivity reactions, all patients treated with paclitaxel should be premedicated with corticosteroids (such as dexamethasone), diphenhydramine and H2 antagonists (such as cimetidine or ranitidine). Minor symptoms such as flushing, skin reactions, dyspnea, hypotension, or tachycardia do not require interruption of therapy. However, severe reactions, such as hypotension requiring treatment, dyspnea requiring bronchodilators, angioedema, or generalized urticaria require immediate discontinuation of paclitaxel and aggressive symptomatic therapy. Patients who have developed severe hypersensitivity reactions should not be rechallenged with paclitaxel.

Cardiovascular:

Hypotension, bradycardia, and hypertension have been observed during administration of Paclitaxel Injection, USP, but generally do not require treatment. Occasionally paclitaxel infusions must be interrupted or discontinued because of initial or recurrent hypertension. Frequent vital sign monitoring, particularly during the first hour of paclitaxel infusion, is recommended. Continuous cardiac monitoring is not required except for patients with serious conduction abnormalities. (See WARNINGS section.) When paclitaxel is used in combination with doxorubicin for treatment of metastatic breast cancer, monitoring of cardiac function is recommended. (See ADVERSE REACTIONS.)

Nervous System:

Although the occurrence of peripheral neuropathy is frequent, the development of severe symptomatology is unusual and requires a dose reduction of 20% for all subsequent courses of paclitaxel.

Paclitaxel contains Dehydrated Alcohol USP, 396 mg/mL; consideration should be given to possible CNS and other effects of alcohol. (See PRECAUTIONS: Pediatric Use section.)

Hepatic:

There is limited evidence that the myelotoxicity of Paclitaxel may be exacerbated in patients with serum total bilirubin >2 times ULN (see CLINICAL PHARMACOLOGY). Extreme caution should be exercised when administering Paclitaxel to such patients, with dose reduction as recommended in TABLE 17.

Injection Site Reaction:

Injection site reactions, including reactions secondary to extravasation, were usually mild and consisted of erythema, tenderness, skin discoloration, or swelling at the injection site. These reactions have been observed more frequently with the 24-hour infusion than with the 3-hour infusion. Recurrence of skin reactions at a site of previous extravasation following administration of paclitaxel at a different site, i.e., “recall”, has been reported.

More severe events such as phlebitis, cellulitis, induration, skin exfoliation, necrosis, and fibrosis have been reported. In some cases the onset of the injection site reaction either occurred during a prolonged infusion or was delayed by a week to ten days.

A specific treatment for extravasation reactions is unknown at this time. Given the possibility of extravasation, it is advisable to closely monitor the infusion site for possible infiltration during drug administration.

Carcinogenesis, Mutagenesis, Impairment of Fertility:

The carcinogenic potential of paclitaxel has not been studied.

Paclitaxel has been shown to be clastogenic in vitro (chromosome aberrations in human lymphocytes) and in vivo (micronucleus test in mice). Paclitaxel was not mutagenic in the Ames test of the CHO/HGPRT gene mutation assay.

Administration of paclitaxel prior to and during mating produced impairment of fertility in male and female rats at doses equal to or greater than 1 mg/kg/day (about 0.04 the daily maximum recommended human dose on a mg/m^2 basis). At this dose, paclitaxel caused reduced fertility and reproductive indices, and increased embryo- and fetotoxicity. (See WARNINGS section.)

PREGNANCY

(See WARNINGS section.)

Nursing Mothers:

It is not known whether the drug is excreted in human milk.
Following intravenous administration of carbon-14 labeled paclitaxel to rats on days 9 to 10 postpartum, concentrations of radioactivity in milk were higher than in plasma and declined in parallel with the plasma concentrations. Because many drugs are excreted in human milk and because of the potential for serious adverse reactions in nursing infants, it is recommended that nursing be discontinued when receiving paclitaxel therapy.

Pediatric Use:

The safety and effectiveness of paclitaxel in pediatric patients have not been established.

There have been reports of central nervous system (CNS) toxicity (rarely associated with death) in a clinical trial in pediatric patients in which paclitaxel was infused intravenously over 3 hours at doses ranging from 350 mg/m^2 to 420 mg/m^2. The toxicity is most likely attributable to the high dose of the ethanol component of the Paclitaxel Injection, USP vehicle given over a short infusion time. The use of concomitant antihistamines may intensify this effect. Although a direct effect of the paclitaxel itself cannot be discounted, the high doses used in this study (over twice the recommended adult dosage) must be considered in assessing the safety of paclitaxel for use in this population.

Geriatric Use:

Of 2228 patients who received paclitaxel in 8 clinical studies evaluating its safety and effectiveness in the treatment of advanced ovarian cancer, breast carcinoma, or NSCLC, and 1570 patients who were randomized to receive paclitaxel in the adjuvant breast cancer study, 649 patients (17%) were 65 years or older and 49 patients (1%) were 75 years or older. In most studies, severe myelosuppression was more frequent in elderly patients; in some studies, severe neuropathy was more common in elderly patients. In 2 clinical studies in NSCLC, the elderly patients treated with paclitaxel had a higher incidence of cardiovascular events. Estimates of efficacy appeared similar in elderly patients and in younger patients; however, comparative efficacy cannot be determined with confidence due to the small number of elderly patients studied. In a study of first-line treatment of ovarian cancer, elderly patients had a lower median survival than younger patients, but no other efficacy parameters favored the younger group. Table 9 presents the incidences of Grade IV neutropenia and severe neuropathy in clinical studies according to age.

Table 9. Selected Adverse Events in Geriatric Patients Receiving Paclitaxel in Clinical Studies

Information for Patients:

(See Patient Information Leaflet.)

ADVERSE REACTIONS

Pooled Analysis of Adverse Event Experiences from Single-Agent Studies:

Data in the following table are based on the experience of 812 patients (493 with ovarian carcinoma and 319 with breast carcinoma) enrolled in 10 studies who received single- agent Paclitaxel Injection, USP. Two hundred and seventy-five patients were treated in eight Phase 2 studies with paclitaxel doses ranging from 135 to 300 mg/m^2 administered over 24 hours (in four of these studies, G-CSF was administered as hematopoietic support). Three hundred and one patients were treated in the randomized Phase 3 ovarian carcinoma study which compared two doses (135 or 175 mg/m^2) and two schedules (3 or 24 hours) of paclitaxel. Two hundred and thirty-six patients with breast carcinoma received paclitaxel (135 or 175 mg/m^2) administered over 3 hours in a controlled study.

Table 10. Summarya of Adverse Events in Patients with Solid Tumors Receiving Single-Agent Paclitaxel

None of the observed toxicities were clearly influenced by age.

Disease-Specific Adverse Event Experiences

First-Line Ovary in Combination: For the 1084 patients who were evaluable for safety in the Phase 3 first-line ovary combination therapy studies, Table 11 shows the incidence of important adverse events. For both studies, the analysis of safety was based on all courses of therapy (6 courses for the GOG-111 study and up to 9 courses for the Intergroup study).

Table 11. Frequencya of Important Adverse Events in the Phase 3 First-Line Ovarian Carcinoma Studies

Second-Line Ovary: For the 403 patients who received single-agent Paclitaxel Injection, USP in the Phase 3 second-line ovarian carcinoma study, the following table shows the incidence of important adverse events.

Table 12. Frequencya of Important Adverse Events in the Phase 3 Second- Line Ovarian Carcinoma Study

Myelosuppression was dose and schedule related, with the schedule effect being more prominent. The development of severe hypersensitivity reactions (HSRs) was rare; 1% of the patients and 0.2% of the courses overall. There was no apparent dose or schedule effect seen for the HSRs. Peripheral neuropathy was clearly dose-related, but schedule did not appear to affect the incidence

Adjuvant Breast:

For the Phase 3 adjuvant breast carcinoma study, the following table shows the incidence of important severe adverse events for the 3121 patients (total population) who were evaluable for safety as well as for a group of 325 patients (early population) who, per the study protocol, were monitored more intensively than other patients.

Table 13. Frequencya of Important Severeb Adverse Events in the Phase 3 Adjuvant Breast Carcinoma Study

The incidence of an adverse event for the total population likely represents an underestimation of the actual incidence given that safety data were collected differently based on enrollment cohort. However, since safety data were collected consistently across regimens, the safety of the sequential addition of paclitaxel following AC therapy may be compared with AC therapy alone. Compared to patients who received AC alone, patients who received AC followed by paclitaxel experienced more Grade III/IV neurosensory toxicity, more Grade III/IV myalgia/arthralgia, more Grade III/IV neurologic pain (5% vs 1%), more Grade III/IV flu-like symptoms (5% vs 3%), and more Grade III/IV hyperglycemia (3% vs 1%). During the additional 4 courses of treatment with paclitaxel, 2 deaths (0.1%) were attributed to treatment. During paclitaxel treatment, Grade IV neutropenia was reported for 15% of patients, Grade II/III neurosensory toxicity for 15%, Grade II/III myalgias for 23%, and alopecia for 46%.

The incidences of severe hematologic toxicities, infections, mucositis, and cardiovascular events increased with higher doses of doxorubicin.

Breast Cancer After Failure of Initial Chemotherapy: For the 458 patients who received single-agent paclitaxel in the Phase 3 breast carcinoma study, the following table shows the incidence of important adverse events by treatment arm (each arm was administered by a 3-hour infusion).

Table 14. Frequencya of Important Adverse Events in the Phase 3 Study of Breast Cancer after Failure of Initial Chemotherapy or Within 6 Months of Adjuvant Chemotherapy

Myelosuppression and peripheral neuropathy were dose related. There was one severe hypersensitivity reaction (HSR) observed at the dose of 135 mg/m^2.

First-Line NSCLC in Combination: In the study conducted by the Eastern Cooperative Oncology Group (ECOG), patients were randomized to either paclitaxel (T) 135 mg/m^2 as a 24-hour infusion in combination with cisplatin (c) 75 mg/m^2, paclitaxel (T) 250 mg/m^2 as a 24-hour infusion in combination with cisplatin (c) 75 mg/m^2 with G- CSF support, or cisplatin (c) 75 mg/m^2 on day 1, followed by etoposide (VP) 100 mg/m^2 on days 1, 2, and 3 (control).

The following table shows the incidence of important adverse events.

Table 15. Frequencya of Important Adverse Events in the Phase 3 Study for First-Line NSCLC

Toxicity was generally more severe in the high-dose paclitaxel treatment arm (T250/c75) than in the low-dose paclitaxel arm (T135/c75). Compared to the cisplatin/etoposide arm, patients in the low-dose paclitaxel arm experienced more arthralgia/myalgia of any grade and more severe neutropenia. The incidence of febrile neutropenia was not reported in this study.

Kaposis & Sarcoma:

The following table shows the frequency of important adverse events in the 85 patients with KS treated with 2 different single-agent paclitaxel regimens.

Table 16. Frequencya of Important Adverse Events in the Aids-Related Kaposi’s Sarcoma Studies

As demonstrated in this table, toxicity was more pronounced in the study utilizing paclitaxel at a dose of 135 mg/m^2 every 3 weeks than in the study utilizing paclitaxel at a dose of 100 mg/m^2 every 2 weeks. Notably, severe neutropenia (76% vs 35%), febrile neutropenia (55% vs 9%), and opportunistic infections (76% vs 54%) were more common with the former dose and schedule. The differences between the 2 studies with respect to dose escalation and use of hematopoietic growth factors, as described above, should be taken into account. (See CLINICAL STUDIES: AIDS-Related Kaposi’s Sarcoma.) Note also that only 26% of the 85 patients in these studies received concomitant treatment with protease inhibitors, whose effect on paclitaxel metabolism has not yet been studied.

Adverse Event Experiences by Body System:

The following discussion refers to the overall safety database of 812 patients with solid tumors treated with single-agent paclitaxel in clinical studies. Toxicities that occurred with greater severity or frequency in previously untreated patients with ovarian carcinoma or NSCLC who received paclitaxel in combination with cisplatin or in patients with breast cancer who received paclitaxel after doxorubicin/cyclophosphamide in the adjuvant setting and that occurred with a difference that was clinically significant in these populations are also described.

The frequency and severity of important adverse events for the Phase 3 ovarian carcinoma, breast carcinoma, NSCLC, and the Phase 2 Kaposi’s sarcoma carcinoma studies are presented above in tabular form by treatment arm. In addition, rare events have been reported from postmarketing experience or from other clinical studies. The frequency and severity of adverse events have been generally similar for patients receiving paclitaxel for the treatment of ovarian, breast, or lung carcinoma or Kaposi’s sarcoma, but patients with AIDS-related Kaposi’s sarcoma may have more frequent and severe hematologic toxicity, infections (including opportunistic infections, see Table 16), and febrile neutropenia. These patients require a lower dose intensity and supportive care. (See CLINICAL STUDIES: AIDS-Related Kaposi’s Sarcoma.) Toxicities that were observed only in or were noted to have occurred with greater severity in the population with Kaposi’s sarcoma and that occurred with a difference that was clinically significant in this population are described. Elevated liver function tests and renal toxicity have a higher incidence in KS patients as compared to patients with solid tumors.

Hematologic:

Bone marrow suppression was the major dose-limiting toxicity of paclitaxel. Neutropenia, the most important hematologic toxicity, was dose and schedule dependent and was generally rapidly reversible. Among patients treated in the Phase 3 second line ovarian study with a 3-hour infusion, neutrophil counts declined below 500 cells/mm3 in 14% of the patients treated with a dose of 135 mg/m^2 compared to 27% at a dose of 175 mg/m^2 (p=0.05). In the same study, severe neutropenia (<500 cells/mm^3) was more frequent with the 24-hour than with the 3-hour infusion; infusion duration had a greater impact on myelosuppression than dose. Neutropenia did not appear to increase with cumulative exposure and did not appear to be more frequent nor more severe for patients previously treated with radiation therapy.

In the study where paclitaxel was administered to patients with ovarian carcinoma at a dose of 135 mg/m^2/24 hours in combination with cisplatin versus the control arm of cyclophosphamide plus cisplatin, the incidences of grade IV neutropenia and of febrile neutropenia were significantly greater in the paclitaxel plus cisplatin arm than in the control arm. Grade IV neutropenia occurred in 81% on the paclitaxel plus cisplatin arm versus 58% on the cyclophosphamide plus cisplatin arm, and febrile neutropenia occurred in 15% and 4% respectively. On the paclitaxel/cisplatin arm, there were 35/1074 (3%) courses with fever in which Grade IV neutropenia was reported at some time during the course. When paclitaxel followed by cisplatin was administered to patients with advanced NSCLC in the ECOG study, the incidences of Grade IV neutropenia were 74% (paclitaxel 135 mg/m^2/24 hours followed by cisplatin) and 65% (paclitaxel 250 mg/m^2/24 hours followed by cisplatin and G-CSF) compared with 55% in patients who received cisplatin/etoposide.

Fever was frequent (12% of all treatment courses). Infectious episodes occurred in 30% of all patients and 9% of all courses; these episodes were fatal in 1% of a l patients, and included sepsis, pneumonia and peritonitis. In the Phase 3 second-line ovarian study, infectious episodes were reported in 20% and 26% of the patients treated with a dose of 135 mg/m^2 or 175 mg/m^2 given as a 3-hour infusion respectively. Urinary tract infections and upper respiratory tract infections were the most frequently reported infectious complications. In the immunosuppressed patient population with advanced HIV disease and poor-risk AIDS-related Kaposi’s sarcoma, 61% of the patients reported at least one opportunistic infection. (See CLINICAL STUDIES: AIDS-Related Kaposi’s Sarcoma.) The use of supportive therapy, including G-CSF, is recommended for patients who have experienced severe neutropenia. (See DOSAGE AND ADMINISTRATION.)

Thrombocytopenia was reported. Twenty percent of the patients experienced a drop in their platelet count below 100,000 cells/mm^3 at least once while on treatment; 7% had a platelet count <50,000 cells/mm3 at the time of their worst nadir. Bleeding episodes were reported in 4% of all courses and by 14% of all patients but most of the hemorrhagic episodes were localized and the frequency of these events was unrelated to the Paclitaxel Injection, USP dose and schedule. In the Phase 3 second-line ovarian study, bleeding episodes were reported in 10% of the patients; no patients treated with the 3-hour infusion received platelet transfusions. In the adjuvant breast carcinoma trial, the incidence of severe thrombocytopenia and platelet transfusions increased with higher doses of doxorubicin.

Anemia (Hb <11 g/dL) was observed in 78% of all patients and was severe (Hb <8 g/dL) in 16% of the cases. No consistent relationship between dose or schedule and the frequency of anemia was observed. Among all patients with normal baseline hemoglobin, 69% became anemic on study but only 7% had severe anemia. Red cell transfusions were required in 25% of all patients and in 12% of those with normal baseline hemoglobin levels.

Hypersensitivity Reactions (HSRs):

All patients received premedication prior to paclitaxel (see WARNINGS and PRECAUTIONS: Hypersensitivity Reactions sections). The frequency and severity of HSRs were not affected by the dose or schedule of paclitaxel administration. In the Phase 3 second-line ovarian study, the 3-hour infusion was not associated with a greater increase in HSRs when compared to the 24-hour infusion. Hypersensitivity reactions were observed in 20% of all courses and in 41% of all patients. These reactions were severe in less than 2% of the patients and 1% of the courses. No severe reactions were observed after course 3 and severe symptoms occurred generally within the first hour of paclitaxel infusion. The most frequent symptoms observed during these severe reactions were dyspnea, flushing, chest pain, and tachycardia. Abdominal pain, pain in the extremities, diaphoresis, and hypertension were also noted.

The minor hypersensitivity reactions consisted mostly of flushing (28%), rash (12%), hypotension (4%), dyspnea (2%), tachycardia (2%), and hypertension (1%). The frequency of hypersensitivity reactions remained relatively stable during the entire treatment period.

Chills, shock, and back pain in association with hypersensitivity reactions have been reported.

Cardiovascular:

Hypotension, during the first 3 hours of infusion, occurred in 12% of all patients and 3% of all courses administered. Bradycardia, during the first 3 hours of infusion, occurred in 3% of all patients and 1% of all courses. In the Phase 3 second-line ovarian study, neither dose nor schedule had an effect on the frequency of hypotension and bradycardia. These vital sign changes most often caused no symptoms and required neither specific therapy nor treatment discontinuation. The frequency of hypotension and bradycardia were not influenced by prior anthracycline therapy.

Significant cardiovascular events possibly related to single-agent paclitaxel occurred in approximately 1% of all patients. These events included syncope, rhythm abnormalities, hypertension and venous thrombosis. One of the patients with syncope treated with paclitaxel at 175 mg/m2over 24 hours had progressive hypotension and died. The arrhythmias included asymptomatic ventricular tachycardia, bigeminy and complete AV block requiring pacemaker placement. Among patients with NSCLC treated with paclitaxel in combination with cisplatin in the Phase 3 study, significant cardiovascular events occurred in 12 to 13%. This apparent increase in cardiovascular events is possibly due to an increase in cardiovascular risk factors in patients with lung cancer.

Electrocardiogram (ECG) abnormalities were common among patients at baseline. ECG abnormalities on study did not usually result in symptoms, were not dose-limiting, and required no intervention. ECG abnormalities were noted in 23% of all patients. Among patients with a normal ECG prior to study entry, 14% of all patients developed an abnormal tracing while on study. The most frequently reported ECG modifications were non-specific repolarization abnormalities, sinus bradycardia, sinus tachycardia, and premature beats. Among patients with normal ECGs at baseline, prior therapy with anthracyclines did not influence the frequency of ECG abnormalities.

Cases of myocardial infarction have been reported. Congestive heart failure, including cardiac dysfunction and reduction of left ventricular ejection fraction or ventricular failure, has been reported typically in patients who have received other chemotherapy, notably anthracyclines. (See PRECAUTIONS: Drug Interactions section.)

Atrial fibrillation and supraventricular tachycardia have been reported.

Respiratory:

Interstitial pneumonia, lung fibrosis, and pulmonary embolism have been reported. Radiation pneumonitis has been reported in patients receiving concurrent radiotherapy.

Pleural effusion and respiratory failure have been reported.

Neurologic:

The assessment of neurologic toxicity was conducted differently among the studies as evident from the data reported in each individual study (see Tables 10- 16). Moreover, the frequency and severity of neurologic manifestations were influenced by prior and/or concomitant therapy with neurotoxic agents.

In general, the frequency and severity of neurologic manifestations were dose- dependent in patients receiving single-agency paclitaxel. Peripheral neuropathy was observed in 60% of all patients (3% severe) and in 52% (2% severe) of the patients without pre-existing neuropathy. The frequency of peripheral neuropathy increased with cumulative dose. Paresthesia commonly occurs in the form of hyperesthesia. Neurologic symptoms were observed in 27% of the patients after the first course of treatment and in 34%-51% from course 2 to 10. Peripheral neuropathy was the cause of paclitaxel discontinuation in 1% of all patients. Sensory symptoms have usually improved or resolved within several months of paclitaxel discontinuation. Pre-existing neuropathies resulting from prior therapies are not a contraindication for paclitaxel therapy.

In the Intergroup first-line ovarian carcinoma study (see Table 11), neurotoxicity included reports of neuromotor and neurosensory events. The regimen with paclitaxel 175 mg/m^2 given by 3-hour infusion plus cisplatin 75 mg/m^2 resulted in greater incidence and severity of neurotoxicity than the regimen containing cyclophosphamide and cisplatin, 87% (21% severe) versus 52% (2% severe), respectively. The duration of grade III or IV neurotoxicity cannot be determined with precision for the Intergroup study since the resolution dates of adverse events were not collected in the case report forms for this trial and complete follow-up documentation was available only in a minority of these patients. In the GOG first-line ovarian carcinoma study, neurotoxicity was reported as peripheral neuropathy. The regimen with paclitaxel 135 mg/m^2 given by 24-hour infusion plus cisplatin 75 mg/m^2 resulted in an incidence of neurotoxicity that was similar to the regimen containing cyclophosphamide plus cisplatin, 25% (3% severe) versus 20% (0% severe), respectively. Cross-study comparison of neurotoxicity in the Intergroup and GOG trials suggests that when paclitaxel is given in combination with cisplatin 75 mg/m^2, the incidence of severe neurotoxicity is more common at a paclitaxel dose of 175 mg/m^2 given by 3-hour infusion (21%) than at a dose of 135 mg/m^2 given by 24-hour infusion (3%).

In patients with NSCLC, administration of paclitaxel followed by cisplatin resulted in a greater incidence of severe neurotoxicity compared to the incidence in patients with ovarian or breast cancer treated with single-agent paclitaxel. Severe neurosensory symptoms were noted in 13% of NSCLC patients receiving paclitaxel 135 mg/m^2 by 24- hour infusion followed by cisplatin 75 mg/m^2 and 8% of NSCLC patients receiving cisplatin/etoposide (see Table 15).

Other than peripheral neuropathy, serious neurologic events following paclitaxel administration have been rare (<1%) and have included grand mal seizures, syncope, ataxia, and neuroencephalopathy.

Autonomic neuropathy resulting in paralytic ileus have been reported. Optic nerve and/or visual disturbances (scintillating scotomata) have also been reported, particularly in patients who have received higher doses than those recommended. These effects generally have been reversible. However, rare reports in the literature of abnormal visual evoked potentials in patients have suggested persistent optic nerve damage.

Postmarketing reports of ototoxicity (hearing loss and tinnitus) have also been received.

Convulsions, dizziness, and headache have been reported.

Arthralgia/Myalgia:

There was no consistent relationship between dose or schedule of paclitaxel and the frequency or severity of arthralgia/myalgia. Sixty percent of all patients treated experienced arthralgia/myalgia; 8% experienced severe symptoms. The symptoms were usually transient, occurred two or three days after paclitaxel administration, and resolved within a few days. The frequency and severity of musculoskeletal symptoms remained unchanged throughout the treatment period.

Hepatic:

No relationship was observed between liver function abnormalities and either dose or schedule of paclitaxel administration. Among patients with normal baseline liver function 7%, 22%, and 19% had elevations in bilirubin, alkaline phosphatase, and AST (SGOT), respectively. Prolonged exposure to paclitaxel was not associated with cumulative hepatic toxicity.

Hepatic necrosis and hepatic encephalopathy leading to death have reported.

Renal:

Among the patients treated for Kaposi’s sarcoma with paclitaxel, 5 patients had renal toxicity of grade III or IV severity. One patient with suspected HIV nephropathy of grade IV severity had to discontinue therapy. The other 4 patients had renal insufficiency with reversible elevations of serum creatinine.

Patients with gynecological cancers treated with paclitaxel and cisplatin may have an increased risk of renal failure with the combination therapy of paclitaxel and cisplatin in gynecological cancers as compared to cisplatin alone.

Gastrointestinal (GI):

Nausea/vomiting, diarrhea, and mucositis were reported by 52%, 38%, and 31% of all patients, respectively. These manifestations were usually mild to moderate. Mucositis was schedule dependent and occurred more frequently with the 24-hour than with the 3-hour infusion.

In patients with poor-risk AIDS-related Kaposi’s sarcoma, nausea/vomiting, diarrhea, and mucositis were reported by 69%, 79%, and 28% of patients, respectively. One-third of 43 patients with Kaposi’s sarcoma complained of diarrhea prior to study start. (See CLINICAL STUDIES: AIDS-Related Kaposi’s Sarcoma.)

In the first-line Phase 3 ovarian carcinoma studies, the incidence of nausea and vomiting when paclitaxel was administered in combination with cisplatin appeared to be greater compared with the database for single-agent paclitaxel in ovarian and breast carcinoma. In addition, diarrhea of any grade was reported more frequently compared to the control arm, but there was no difference for severe diarrhea in these studies.

Intestinal obstruction, intestinal perforation, pancreatitis, ischemic colitis, and dehydration have been reported. Neutropenic enterocolitis (typhlitis), despite the coadministration of G-CSF, were observed in patients treated with paclitaxel alone and in combination with other chemotherapeutic agents.

Injection Site Reaction:

Injection site reactions, including reactions secondary to extravasation, were usually mild and consisted of erythema, tenderness, skin discoloration, or swelling at the injection site. These reactions have been observed more frequently with the 24-hour infusion than with the 3-hour infusion. Recurrence of skin reactions at a site of previous extravasation following administration of paclitaxel at a different site, i.e., “recall”, has been reported.
More severe events such as phlebitis, cellulitis, induration, skin exfoliation, necrosis, and fibrosis have been reported. In some cases the onset of the injection site reaction either occurred during a prolonged infusion or was delayed by a week to ten days.

A specific treatment for extravasation reactions is unknown at this time. Given the possibility of extravasation, it is advisable to closely monitor the infusion site for possible infiltration during drug administration.

Other Clinical Events:

Alopecia was observed in almost all (87%) of the patients. Transient skin changes due to Paclitaxel Injection, USP-related hypersensitivity reactions have been observed, but no other skin toxicities were significantly associated with paclitaxel administration. Nail changes (changes in pigmentation or discoloration of nail bed) were uncommon (2%). Edema was reported in 21% of all patients (17% of those without baseline edema); only 1% had severe edema and none of these patients required treatment discontinuation. Edema was most commonly focal and disease- related. Edema was observed in 5% of all courses for patients with normal baseline and did not increase with time on study.

Skin abnormalities related to radiation recall as we l as reports of maculopapular rash, pruritus, Stevens-Johnson syndrome, and toxic epidermal necrolysis have been reported. In postmarketing experience, diffuse edema, thickening, and sclerosing of the skin have been reported following paclitaxel administration. Paclitaxel has been reported to exacerbate signs and symptoms of scleroderma.

Reports of asthenia and malaise have been received as part of the continuing surveillance of paclitaxel safety. In the Phase 3 trial of paclitaxel 135 mg/m^2 over 24 hours in combination with cisplatin as first-line therapy of ovarian cancer, asthenia was reported in 17% of the patients, significantly greater than the 10% incidence observed in the control arm of cyclophosphamide/cisplatin.

Conjunctivitis, increased lacrimation, anorexia, confusional state, photopsia, visual floaters, vertigo, and increase in blood creatinine have been reported.

Accidental Exposure: Upon inhalation, dyspnea, chest pain, burning eyes, sore throat, and nausea have been reported. Following topical exposure, events have included tingling, burning, and redness.

OVERDOSAGE

There is no known antidote for paclitaxel overdosage. The primary anticipated complications of overdosage would consist of bone marrow suppression, peripheral neurotoxicity, and mucositis. Overdoses in pediatric patients may be associated with acute ethanol toxicity (see PRECAUTIONS: Pediatric Use section).

DOSAGE & ADMINISTRATION

NOTE: Contact of the undiluted concentrate with plasticized PVC equipment or devices used to prepare solutions for infusion is not recommended. In order to minimize patient exposure to the plasticizer DEHP [di-(2-ethylhexyl)phthalate], which may be leached from PVC infusion bags or sets, diluted paclitaxel solutions should be stored in bottles (glass, polypropylene) or plastic bags (polypropylene, polyolefin) and administered through polyethylene-lined administration sets.

All patients should be premedicated prior to paclitaxel administration in order to prevent severe hypersensitivity reactions. Such premedication may consist of dexamethasone 20 mg PO administered approximately 12 and 6 hours before paclitaxel, diphenhydramine (or its equivalent) 50 mg I.V. 30 to 60 minutes prior to paclitaxel, and cimetidine (300 mg) or ranitidine (50 mg) I.V. 30 to 60 minutes before paclitaxel.

For patients with carcinoma of the ovary the following regimen is recommended: (see CLINICAL STUDIES: Ovarian Carcinoma):

1) For previously untreated patients with carcinoma of the ovary, one of the following recommended regimens may be given every 3 weeks. In selecting the appropriate regimen, differences in toxicities should be considered (see Table 11 in ADVERSE REACTIONS: Disease-Specific Adverse Event Experiences).

a. Paclitaxel administered intravenously over 3 hours at a dose of 175 mg/m^2 followed by cisplatin at a dose of 75 mg/m^2; or

b. Paclitaxel administered intravenously over 24 hours at a dose of 135 mg/m^2 followed by cisplatin at a dose of 75 mg/m^2.

2) In patients previously treated with chemotherapy for carcinoma of the ovary, paclitaxel has been used at several doses and schedules; however, the optimal regimen is not yet clear. (See CLINICAL STUDIES: Ovarian Carcinoma section). The recommended regimen is paclitaxel 135 mg/m^2 or 175 mg/m^2 administered intravenously over 3 hours every 3 weeks.

For patients with carcinoma of the breast, the following is recommended (see CLINICAL STUDIES: Breast Carcinoma section):

1) For the adjuvant treatment of node-positive breast cancer, the recommended regimen is paclitaxel, at a dose of 175 mg/m^2 intravenously over 3 hours every 3 weeks for 4 courses administered sequentially to doxorubicin-containing combination chemotherapy. The clinical trial used 4 courses of doxorubicin and cyclophosphamide (see CLINICAL STUDIES: Breast Carcinoma).

2) After failure of initial chemotherapy for metastatic disease or relapse within 6 months of adjuvant chemotherapy, paclitaxel at a dose of 175 mg/m^2 administered intravenously over 3 hours every 3 weeks has been shown to be effective.

For patients with non-small cell lung carcinoma, the recommended regimen, given every 3 weeks, is paclitaxel administered intravenously over 24 hours at a dose of 135 mg/m^2 followed by cisplatin, 75 mg/m^2.

For patients with AIDS-related Kaposi’s sarcoma, paclitaxel administered at a dose of 135 mg/m^2 given intravenously over 3 hours every 3 weeks or at a dose of 100 mg/m^2 given intravenously over 3 hours every 2 weeks is recommended (dose intensity 45–50 mg/m^2/week). In the 2 clinical trials evaluating these schedules (see CLINICAL STUDIES: AIDS-Related Kaposi’s Sarcoma), the former schedule (135 mg/m^2 every 3 weeks) was more toxic than the latter. In addition, all patients with low performance status were treated with the latter schedule (100 mg/m^2 every 2 weeks).

Based upon the immunosuppression in patients with advanced HIV disease, the following modifications are recommended in these patients:

1) Reduce the dose of dexamethasone as 1 of the 3 premedication drugs to 10 mg PO (instead of 20 mg PO);

2) Initiate or repeat treatment with paclitaxel only if the neutrophil count is at least 1,000 cells/mm^3;

3) Reduce the dose of subsequent courses of paclitaxel by 20% for patients who experience severe neutropenia (neutrophil <500 cells/mm^3 for a week or longer); and4) Initiate concomitant hematopoietic growth factor (G-CSF) as clinically indicated.

For the therapy of patients with solid tumors (ovary, breast and NSCLC), courses of paclitaxel should not be repeated until the neutrophil count is at least 1,500 cells/mm^3 and the platelet count is at least 100,000 cells/mm^3. Paclitaxel should not be given to patients with AIDS-related Kaposi’s sarcoma if the baseline or subsequent neutrophil count is less than 1,000 cells/mm^3. Patients who experience severe neutropenia (neutrophil <500 cells/mm3 for a week or longer) or severe peripheral neuropathy during Paclitaxel Injection, USP therapy should have dosage reduced by 20% for subsequent courses of paclitaxel. The incidence of neurotoxicity and the severity of neutropenia increase with dose.

Hepatic Impairment: Patients with hepatic impairment may be at increased risk of toxicity, particularly grade III–IV myelosuppression (see CLINICAL PHARMACOLOGY and PRECAUTIONS: Hepatic). Recommendations for dosage adjustment for the first course of therapy are shown in Table 17 for both 3- and 24- hour infusions. Further dose reduction in subsequent courses should be based on individual tolerance. Patients should be monitored closely for the development of profound myelosuppression.

Table 17. Recommendations for Dosing in Patients with Hepatic Impairment Based on Clinical Trial Dataa

Preparation and Administration Precautions: Procedures for proper handling and disposal of anticancer drugs should be considered. Several guidelines on this subject have been published.1–4 To minimize the risk of dermal exposure, always wear impervious gloves when handling vials containing paclitaxel Injection. If paclitaxel solution contacts the skin, wash the skin immediately and thoroughly with soap and water. Following topical exposure, events have included tingling, burning, and redness. If paclitaxel contacts mucous membranes, the membranes should be flushed thoroughly with water. Upon inhalation, dyspnea, chest pain, burning eyes, sore throat, and nausea have been reported.

Given the possibility of extravasation, it is advisable to closely monitor the infusion site for possible infiltration during drug administration. (See PRECAUTIONS: Injection Site Reaction section.)

Preparation for Intravenous Administration: Paclitaxel must be diluted prior to infusion. Paclitaxel should be diluted in 0.9% Sodium Chloride Injection, USP; 5% Dextrose Injection, USP; 5% Dextrose and 0.9% Sodium Chloride Injection, USP or 5% Dextrose in Ringer’s Injection to a final concentration of 0.3 to 1.2 mg/mL. The solutions are physically and chemically stable for up to 27 hours at ambient temperature (approximately 25°C) and room lighting conditions. Parenteral drug products should be inspected visually for particulate matter and discoloration prior to administration whenever solution and container permit.

Upon preparation, solutions may show haziness, which is attributed to the formulation vehicle. No significant losses in potency have been noted following simulated delivery of the solution through I.V. tubing containing an in-line (0.22 micron) filter.

Data collected for the presence of the extractable plasticizer DEHP [di-(2-ethylhexyl) phthalate] show that levels increase with time and concentration when dilutions are prepared in PVC containers. Consequently, the use of plasticized PVC containers and administration sets is not recommended.

Paclitaxel solutions should be prepared and stored in glass, polypropylene, or polyolefin containers. Non-PVC containing administration sets, such as those which are polyethylene-lined, should be used.

Paclitaxel should be administered through an in-line filter with a microporous membrane not greater than 0.22 microns. Use of filter devices such as IVEX-2® filters which incorporate short inlet and outlet PVC-coated tubing has not resulted in significant leaching of DEHP.

The Chemo Dispensing Pin™ device or similar devices with spikes should not be used with vials of paclitaxel since they can cause the stopper to collapse resulting in loss of sterile integrity of the paclitaxel solution.

Stability: Unopened vials of Paclitaxel Injection, USP are stable until the date indicated on the package when stored between 20° to 25°C (68° to 77°F), in the original package. Neither freezing nor refrigeration adversely affects the stability of the product. Upon refrigeration components in the paclitaxel vial may precipitate, but will redissolve upon reaching room temperature with little or no agitation. There is no impact on product quality under these circumstances. If the solution remains cloudy or if an insoluble precipitate is noted, the vial should be discarded. Solutions for infusion prepared as recommended are stable at ambient temperature (approximately 25°C) and lighting conditions for up to 27 hours.

HOW SUPPLIED

Paclitaxel Injection, USP (6 mg/mL) is supplied in the following:

Unit of Sale | Concentration
NDC 69339-227-05 Carton containing 1 multiple- dose vial | 30 mg/5 mL
NDC 69339-228-17 Carton containing 1 multiple- dose vial | 100 mg/16.7 mL
NDC 69339-229-50 Carton containing 1 multiple- dose vial | 300 mg/50 mL

Storage: Store the vials in original cartons between 20° to 25°C (68° to 77°F). [See USP Controlled Room Temperature.] Retain in the original package to protect from light.

Handling and Disposal: See DOSAGE AND ADMINISTRATION: Preparation and Administration Precautions.

REFERENCES

1. NIOSH Alert: Preventing occupational exposures to antineoplastic and other hazardous drugs in healthcare settings. 2004. U.S. Department of Health and Human Services, Public Health Service, Centers for Disease Control and Prevention, National Institute for Occupational Safety and Health, DHHS (NIOSH) Publication No. 2004165.

2.OSHA Technical Manual, TED 1-0.15A, Section VI: Chapter 2. Controlling occupational exposure to hazardous drugs. OSHA, 1999.

http://www.osha.gov/dts/osta/otm/otm_vi/otm_vi_2.html.

3.American Society of Health-System Pharmacists. ASHP guidelines on handling hazardous drugs. Am J Health-Syst Pharm. 2006;63:1172-1193.

4.Polovich M, White JM, Ke leher LO, eds. 2005. Chemotherapy and biotherapy guidelines and recommendations for practice. 2nd ed. Pittsburgh, PA: Oncology Nursing Society.

Manufactured by:

NATCO PHARMA LIMITED

Kothur- 509 228, Telangana, India

Manufactured for:

NATCO Pharma USA LLC,

Parsippany, NJ 07054, USA

Revised: 09/2024

SPL PATIENT PACKAGE INSERT

Paclitaxel Injection, USP
Read this patient information leaflet before you start taking paclitaxel. There may be new information. This information does not take the place of talking to your healthcare provider about your medical condition or your treatment.

What is the most important information I should know about paclitaxel?

Paclitaxel can cause serious side effects including death.
Serious allergic reactions (anaphylaxis) can happen in people who receive paclitaxel.

Anaphylaxis is a serious medical emergency that can lead to death and must be treated right away.

Tel l your healthcare provider right away if you have any of these signs of an allergic reaction:

• trouble breathing
• sudden swelling of your face, lips, tongue, throat, or trouble swallowing
• hives (raised bumps) or rash

Your healthcare provider will give you medicines to lessen your chance of having an allergic reaction.

What is paclitaxel?
Paclitaxel is a prescription medicine used to treat some forms of:

• ovarian cancer
• breast cancer
• lung cancer
• Kaposi’s sarcoma

It is not known if paclitaxel is safe or effective in children.
Who should not receive paclitaxel?
Do not receive paclitaxel if:

• you are allergic to any of the ingredients in paclitaxel. See the end of this leaflet for a complete list of ingredients in paclitaxel.
• are allergic to medicines containing polyoxyethylated castor oil.
• you have low white blood cell counts.

What should I tell my healthcare provider before receiving paclitaxel?

Before receiving paclitaxel, tell your healthcare provider about all your medical conditions, including if you:

• have liver problems
• have heart problems
• are pregnant or plan to become pregnant. paclitaxel can harm your unborn baby. Talk to your healthcare provider if you are pregnant or plan to become pregnant.
• are breast-feeding or plan to breast-feed. It is not known if paclitaxel passes into your breast milk. You and your healthcare provider should decide if you will receive paclitaxel or breast-feed.

Tell your healthcare provider about all the medicines you take, including prescription and non-prescription medicines, vitamins, and herbal supplements.
Know the medicines you take. Keep a list of them and show it to your healthcare provider and pharmacist when you get a new medicine.
How will I receive paclitaxel?
• Paclitaxel is injected into a vein (intravenous [IV] infusion) by your healthcare provider.

Your healthcare provider will do certain tests while you receive paclitaxel.

What are the possible side effects of paclitaxel?
Tel l your healthcare provider right away if you have:

• severe stomach pain
• severe diarrhea

The most common side effects of paclitaxel include:

• low red blood cell count (anemia) feeling weak or tired
• hair loss
• numbness, tingling, or burning in your hands or feet (neuropathy)
• joint and muscle pain
• nausea and vomiting
• hypersensitivity reaction - trouble breathing; sudden swelling of your face, lips, tongue, throat, or trouble swallowing; hives (raised bumps) or rash
• diarrhea
• mouth or lip sores (mucositis)
• infections - if you have a fever (temperature above 100.4°F) or other sign of infection, tell your healthcare provider right away
• swelling of your hands, face, or feet
• bleeding events
• irritation at the injection site
• low blood pressure (hypotension)

Tell your healthcare provider if you have any side effect that bothers you or that does not go away.
These are not all the possible side effects of paclitaxel. For more information, ask your healthcare provider or pharmacist.

To report SUSPECTED ADVERSE REACTIONS, contact NATCO PHARMA LLC at 1-201-786-6500 or FDA at 1-800-FDA-1088 or www.fda.gov/medwatch.

General information about the safe and effective use of paclitaxel.

Medicines are sometimes prescribed for purposes other than those listed in a patient information leaflet. Do not use paclitaxel for a condition for which it was not prescribed.
Do not give paclitaxel to other people, even if they have the same symptoms that you have. It may harm them.
This patient information leaflet summarizes the most important information about paclitaxel. If you would like more information, talk with your healthcare provider. You can ask your pharmacist or healthcare provider for information about paclitaxel that is written for health professionals. For more contact NATCO PHARMA LLC at 1-201-786-6500.

What are the ingredients in paclitaxel?
Active ingredient: paclitaxel.
Inactive ingredients include: Polyoxyl 35 castor oil, NF and dehydrated alcohol, USP and Anhydrous Citric Acid, USP.

What is cancer?
Under normal conditions, the cells in your body divide and grow in an orderly, controlled way. Cell division and growth are necessary for the human body to perform its functions and to repair itself, when necessary. Cancer cells are different from normal cells because they are not able to control their own growth. The reasons for this abnormal growth are not yet fully understood. A tumor is a mass of unhealthy cells that are dividing and growing fast and in an uncontrolled way. When a tumor invades surrounding healthy body tissue, it is known as a malignant tumor. A malignant tumor can spread (metastasize) from its original site to other parts of the body if not found and treated early.

Manufactured by:
NATCO PHARMA LIMITED
Kothur- 509 228, Telangana, India

Manufactured for:
NATCO Pharma USA LLC,
Parsippany, NJ 07054, USA

Revised: 09/2024

PRINCIPAL DISPLAY PANEL - 30mg Label

NDC 69339-227-05

NATCO PHARMA USA

Semisynthetic Paclitaxel Injection, USP

30 mg/5 mL (6 mg/mL)

WARNING: Cytotoxic Agent

Dilution required. Read enclosed package Insert

Sterile
Rx only

Multiple Dose Vial

PRINCIPAL DISPLAY PANEL - 30mg Carton

NDC 69339-227-05

NATCO PHARMA USA

Semisynthetic Paclitaxel Injection, USP
30 mg/ 5 mL (6 mg/mL)

WARNING: Cytotoxic Agent

Dilution required. Read enclosed package Insert

Sterile

Rx only

Multiple-Dose vial

PRINCIPAL DISPLAY PANEL - 100mg Label

NDC 69339-228-17

NATCO PHARMA USA

Semisynthetic Paclitaxel Injection, USP

100 mg/16.7 mL (6 mg/mL)

WARNING: Cytotoxic Agent

Dilution required. Read enclosed package Insert

Sterile
Rx only

Multiple Dose Vial

PRINCIPAL DISPLAY PANEL - 100mg Carton

NDC 69339-228-17

NATCO PHARMA USA

Semisynthetic Paclitaxel Injection, USP
100 mg/ 16.7 mL
(6 mg/mL)

WARNING: Cytotoxic Agent

Dilution required. Read enclosed package Insert

Sterile

Rx only

Multiple-Dose vial

PRINCIPAL DISPLAY PANEL - 300mg Label

NDC 69339-229-50

NATCO PHARMA USA

Semisynthetic Paclitaxel Injection, USP

300 mg/50 mL (6 mg/mL)

WARNING: Cytotoxic Agent

Dilution required. Read enclosed package Insert

Sterile
Rx only

Multiple Dose Vial

PRINCIPAL DISPLAY PANEL - 300 mg Carton

NDC 69339-229-50

NATCO PHARMA USA

Semisynthetic Paclitaxel Injection, USP
300 mg/ 50 mL
(6 mg/mL)

WARNING: Cytotoxic Agent

Dilution required. Read enclosed package Insert

Sterile

Rx only

Multiple-Dose vial